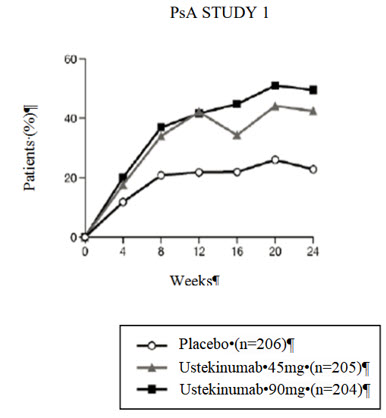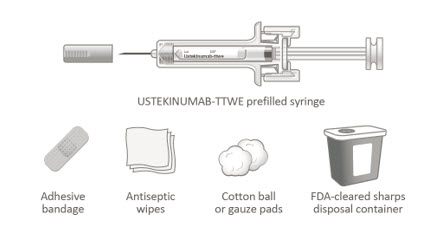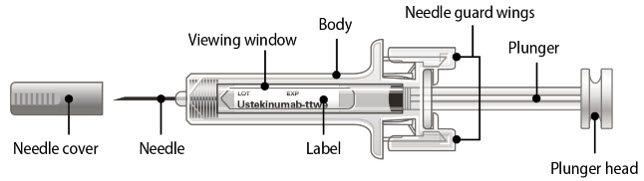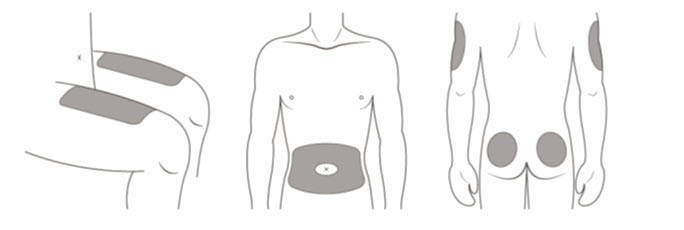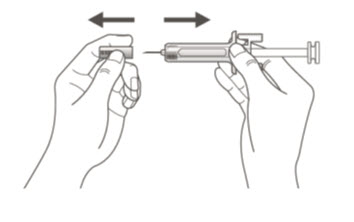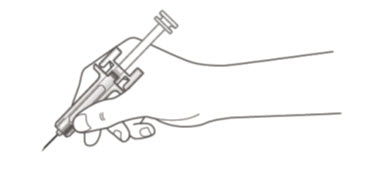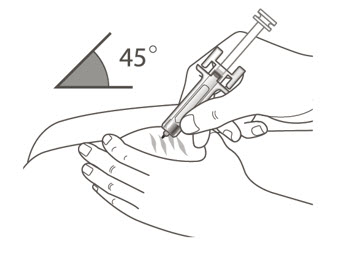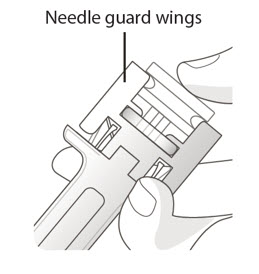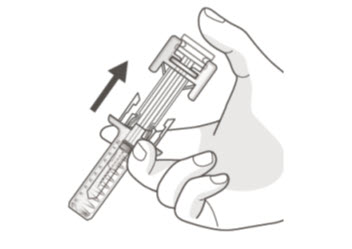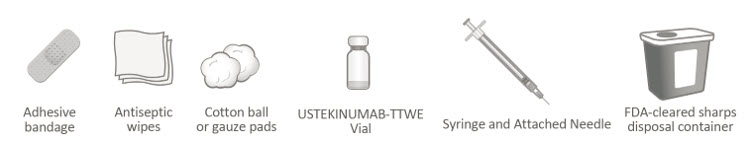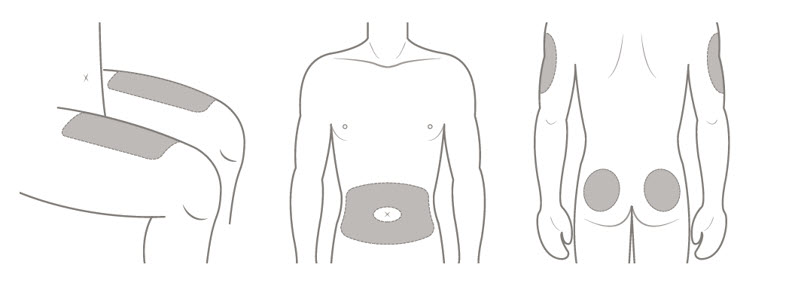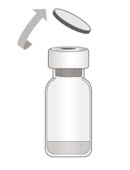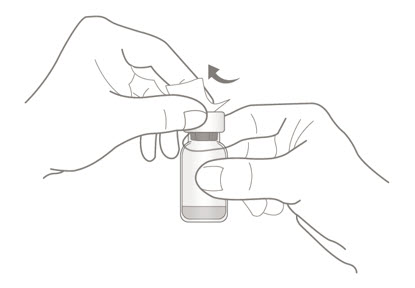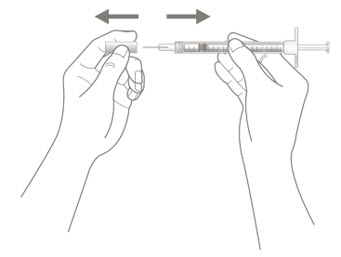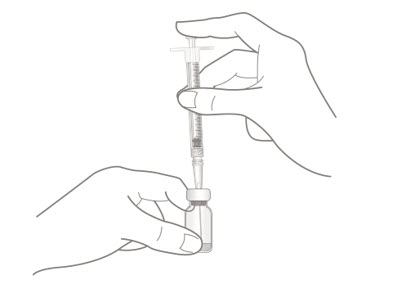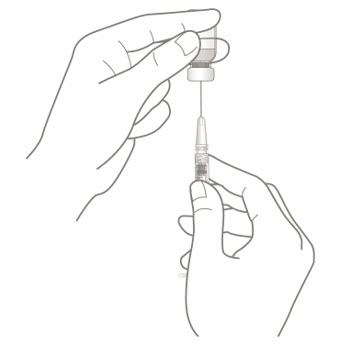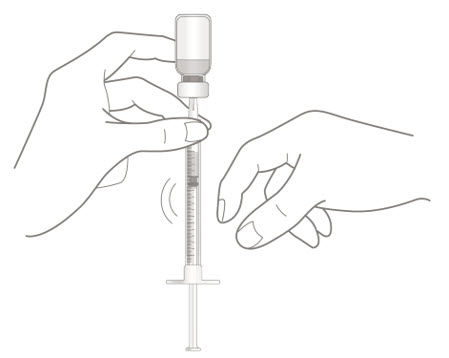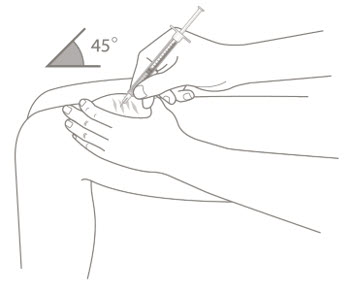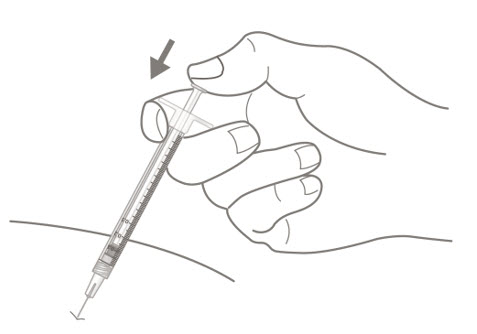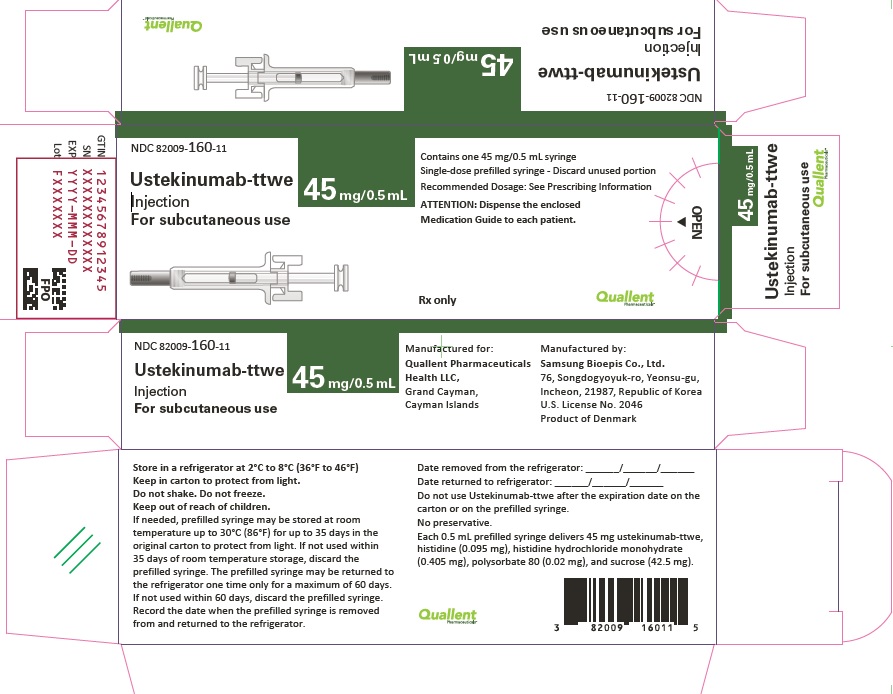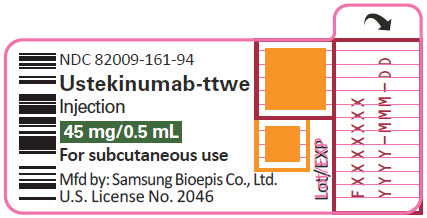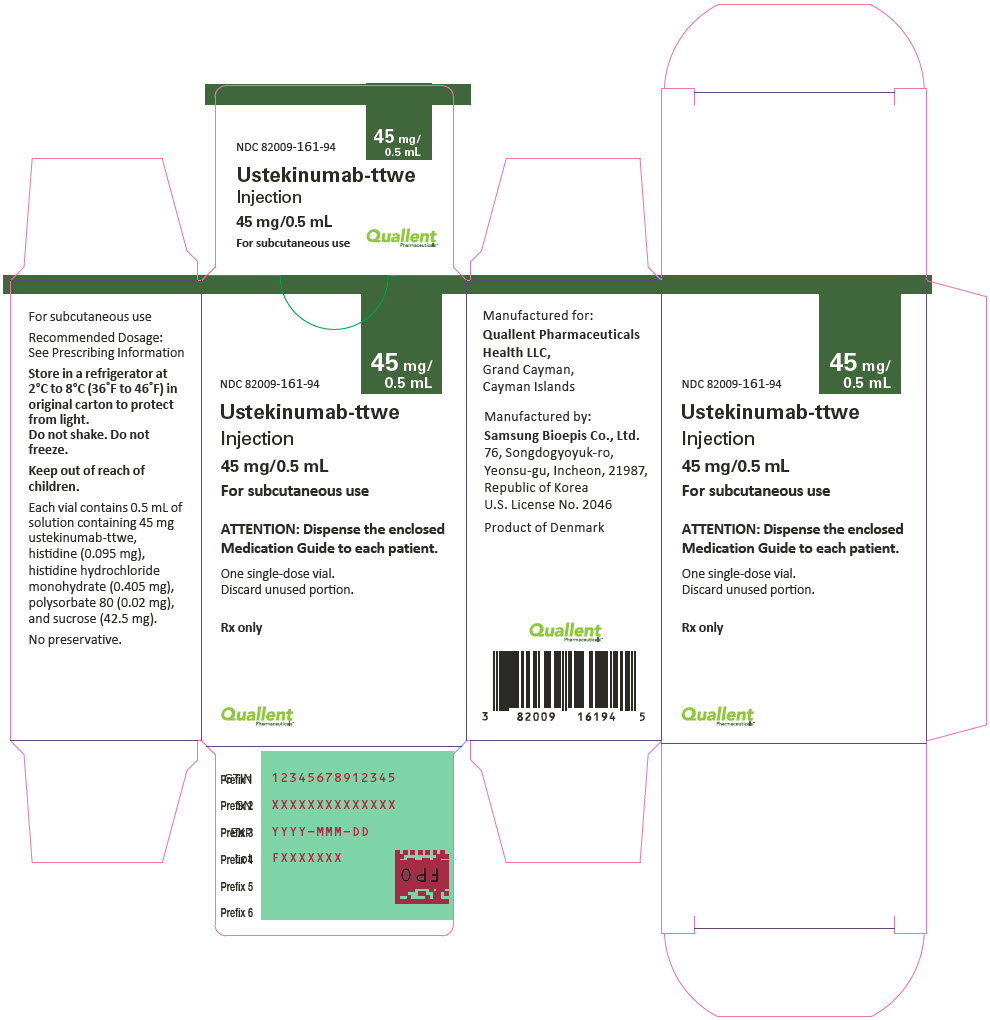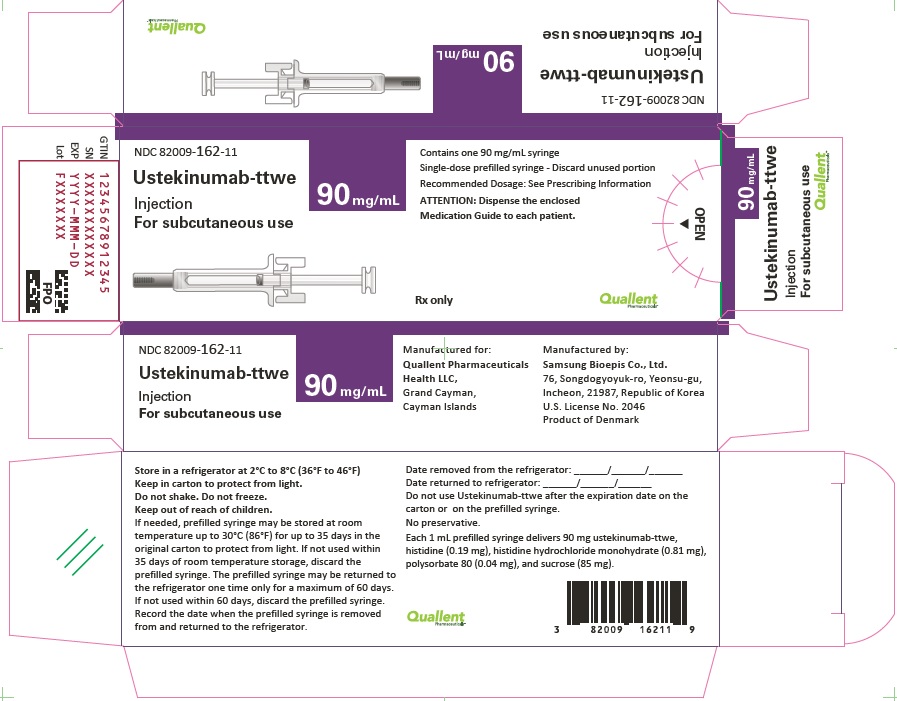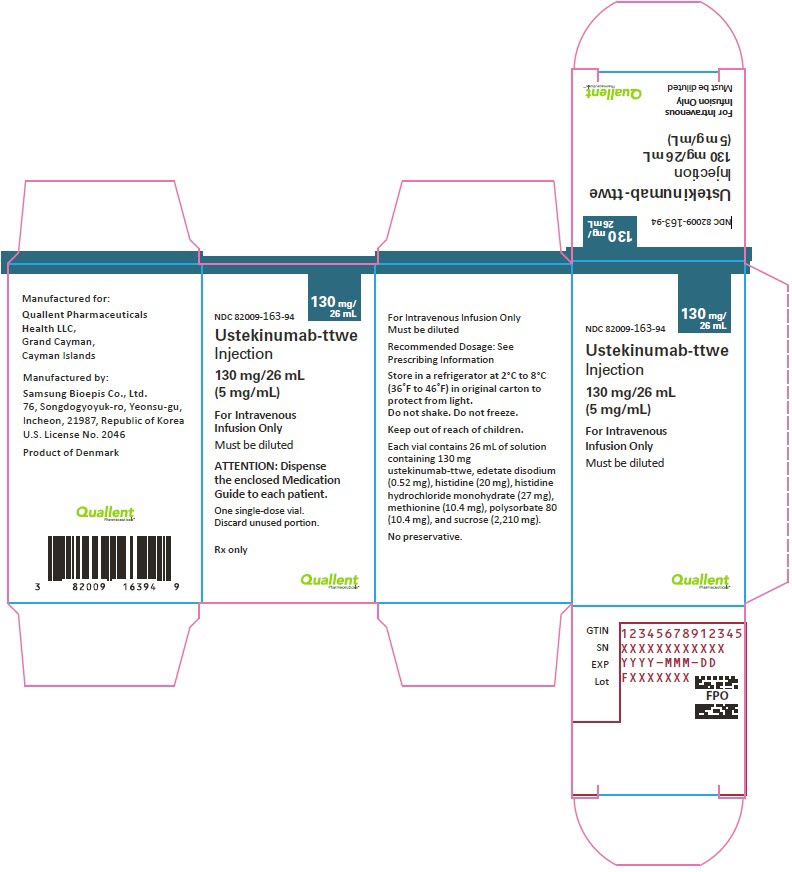 DRUG LABEL: USTEKINUMAB-TTWE
NDC: 82009-160 | Form: INJECTION, SOLUTION
Manufacturer: Quallent Pharmaceuticals Health LLC
Category: prescription | Type: HUMAN PRESCRIPTION DRUG LABEL
Date: 20260112

ACTIVE INGREDIENTS: USTEKINUMAB 45 mg/0.5 mL

HIGHLIGHTS OF PRESCRIBING INFORMATION

These highlights do not include all the information needed to use USTEKINUMAB-TTWE safely and effectively. See full prescribing information for USTEKINUMAB-TTWE.
USTEKINUMAB-TTWE injection, for subcutaneous or intravenous use
Initial U.S. Approval: 2024
Ustekinumab-ttwe is biosimilar [Biosimilar means that the biological product is approved based on data demonstrating that it is highly similar to an FDA-approved biological product, known as a reference product, and that there are no clinically meaningful differences between the biosimilar product and the reference product. Biosimilarity of USTEKINUMAB-TTWE has been demonstrated for the condition(s) of use (e.g., indication(s), dosing regimen(s)), strength(s), dosage form(s), and route(s) of administration described in its Full Prescribing Information] to STELARA (ustekinumab)

RECENT MAJOR CHANGES

Warnings and Precautions, Serious Hypersensitivity Reactions (5.5) | 01/2026

1 INDICATIONS AND USAGE

USTEKINUMAB-TTWE is a human interleukin-12 and -23 antagonist indicated for the treatment of:

Adult patients with:

- moderate to severe plaque psoriasis (PsO) who are candidates for phototherapy or systemic therapy. (1.1)
- active psoriatic arthritis (PsA). (1.2)
- moderately to severely active Crohn's disease (CD). (1.3)
- moderately to severely active ulcerative colitis. (1.4)

Pediatric patients 6 years and older with:

- moderate to severe plaque psoriasis (PsO), who are candidates for phototherapy or systemic therapy. (1.1)
- active psoriatic arthritis (PsA). (1.2)

2 DOSAGE AND ADMINISTRATION

Adult Patients with Plaque Psoriasis Subcutaneous Recommended Dosage (2.1):

Weight Range (kilograms) | Dosage
less than or equal to 100 kg | 45 mg administered subcutaneously initially and 4 weeks later, followed by 45 mg administered subcutaneously every 12 weeks
greater than 100 kg | 90 mg administered subcutaneously initially and 4 weeks later, followed by 90 mg administered subcutaneously every 12 weeks

Pediatric Patients 6 Years of Age and Older with Plaque Psoriasis Subcutaneous Recommended Dosage (2.1):

Weight-based dosing is recommended at the initial dose, 4 weeks later, then every 12 weeks thereafter.

Weight Range (kilograms) | Dose
less than 60 kg | 0.75 mg/kg
60 kg to 100 kg | 45 mg
greater than 100 kg | 90 mg

Psoriatic Arthritis Adult Subcutaneous Recommended Dosage (2.2):

- The recommended dosage is 45 mg administered subcutaneously initially and 4 weeks later, followed by 45 mg administered subcutaneously every 12 weeks.
- For patients with co-existent moderate-to-severe plaque psoriasis weighing greater than 100 kg, the recommended dosage is 90 mg administered subcutaneously initially and 4 weeks later, followed by 90 mg administered subcutaneously every 12 weeks.

Psoriatic Arthritis Pediatric 6 years of Age and Older Subcutaneous Recommended Dosage (2.2): Weight-based dosing is recommended at the initial dose, 4 weeks later, then every 12 weeks thereafter.

Weight Range (kilograms) | Dose
less than 60 kg | 0.75 mg/kg
60 kg or more | 45 mg
greater than 100 kg with co-existent moderate-to-severe plaque psoriasis | 90 mg

Crohn's Disease and Ulcerative Colitis Initial Adult Intravenous Recommended Dose (2.3): A single intravenous infusion using weight-based dosing:

Weight Range (kilograms) | Recommended Dose
up to 55 kg | 260 mg (2 vials)
greater than 55 kg to 85 kg | 390 mg (3 vials)
greater than 85 kg | 520 mg (4 vials)

Crohn's Disease and Ulcerative Colitis Maintenance Adult Subcutaneous Recommended Dosage (2.3): A subcutaneous 90 mg dose 8 weeks after the initial intravenous dose, then every 8 weeks thereafter.

3 DOSAGE FORMS AND STRENGTHS

Subcutaneous Injection (3)

- Injection: 45 mg/0.5 mL or 90 mg/mL solution in a single-dose prefilled syringe
- Injection: 45 mg/0.5 mL solution in a single-dose vial

Intravenous Infusion (3)

- Injection: 130 mg/26 mL (5 mg/mL) solution in a single-dose vial

4 CONTRAINDICATIONS

- Clinically significant hypersensitivity to ustekinumab products or to any of the excipients in USTEKINUMAB-TTWE. (4)

5 WARNINGS AND PRECAUTIONS

- Infections: Serious infections have occurred. Avoid starting USTEKINUMAB-TTWE during any clinically important active infection. If a serious infection or clinically significant infection develops, discontinue USTEKINUMAB-TTWE until the infection resolves. (5.1)
- Theoretical Risk for Particular Infections: Serious infections from mycobacteria, salmonella and Bacillus Calmette-Guerin (BCG) vaccinations have been reported in patients genetically deficient in IL-12/IL-23. Consider diagnostic tests for these infections as dictated by clinical circumstances. (5.2)
- Tuberculosis (TB): Evaluate patients for TB prior to initiating treatment with USTEKINUMAB-TTWE. Initiate treatment of latent TB before administering USTEKINUMAB-TTWE. (5.3)
- Malignancies: Ustekinumab products may increase risk of malignancy. The safety of ustekinumab products in patients with a history of or a known malignancy has not been evaluated. (5.4)
- Serious Hypersensitivity Reactions: If a severe or other clinically significant hypersensitivity reaction occurs, discontinue USTEKINUMAB-TTWE immediately and initiate appropriate medical treatment. (5.5)
- Posterior Reversible Encephalopathy Syndrome (PRES): If PRES is suspected, treat promptly and discontinue USTEKINUMAB-TTWE. (5.6)
- Immunizations: Avoid use of live vaccines in patients during treatment with USTEKINUMAB-TTWE. (5.7)
- Noninfectious Pneumonia: Cases of interstitial pneumonia, eosinophilic pneumonia and cryptogenic organizing pneumonia have been reported during post-approval use of ustekinumab products. If diagnosis is confirmed, discontinue USTEKINUMAB-TTWE and institute appropriate treatment. (5.8)

6 ADVERSE REACTIONS

Most common adverse reactions are:

- Psoriasis and Psoriatic Arthritis (≥3%): nasopharyngitis, upper respiratory tract infection, headache, and fatigue. (6.1)
- Crohn's Disease, induction (≥3%): vomiting. (6.1)
- Crohn's Disease, maintenance (≥3%): nasopharyngitis, injection site erythema, vulvovaginal candidiasis/mycotic infection, bronchitis, pruritus, urinary tract infection, and sinusitis. (6.1)
- Ulcerative colitis, induction (≥3%): nasopharyngitis (6.1)
- Ulcerative colitis, maintenance (≥3%): nasopharyngitis, headache, abdominal pain, influenza, fever, diarrhea, sinusitis, fatigue, and nausea (6.1)

To report SUSPECTED ADVERSE REACTIONS, contact Quallent Pharmaceuticals Health LLC at 1-877-605-7243 or FDA at 1-800-FDA-1088 or www.fda.gov/medwatch.

FULL PRESCRIBING INFORMATION

1 INDICATIONS AND USAGE

1.1 Plaque Psoriasis (PsO)

USTEKINUMAB-TTWE is indicated for the treatment of adults and pediatric patients 6 years of age and older with moderate to severe plaque psoriasis who are candidates for phototherapy or systemic therapy.

1.2 Psoriatic Arthritis (PsA)

USTEKINUMAB-TTWE is indicated for the treatment of adults and pediatric patients 6 years of age and older with active psoriatic arthritis.

1.3 Crohn's Disease (CD)

USTEKINUMAB-TTWE is indicated for the treatment of adult patients with moderately to severely active Crohn's disease.

1.4 Ulcerative Colitis

USTEKINUMAB-TTWE is indicated for the treatment of adult patients with moderately to severely active ulcerative colitis.

2 DOSAGE AND ADMINISTRATION

2.1 Recommended Dosage in Plaque Psoriasis

Subcutaneous Adult Dosage Regimen

- For patients weighing 100 kg or less, the recommended dosage is 45 mg initially and 4 weeks later, followed by 45 mg every 12 weeks.
- For patients weighing more than 100 kg, the recommended dosage is 90 mg initially and 4 weeks later, followed by 90 mg every 12 weeks.

In subjects weighing more than 100 kg, 45 mg was also shown to be efficacious. However, 90 mg resulted in greater efficacy in these subjects [see Clinical Studies (14)].

Subcutaneous Pediatric Dosage Regimen

Administer USTEKINUMAB-TTWE subcutaneously at Weeks 0 and 4, then every 12 weeks thereafter.

The recommended dose of USTEKINUMAB-TTWE for pediatric patients 6 years of age and older with plaque psoriasis based on body weight is shown below (Table 1).

Table 1: Recommended Dose of USTEKINUMAB-TTWE for Subcutaneous Injection in Pediatric Patients 6 Years of Age and Older with Plaque Psoriasis
Body Weight of Patient at the Time of Dosing | Recommended Dose
less than 60 kg | 0.75 mg/kg
60 kg to 100 kg | 45 mg
more than 100 kg | 90 mg

For pediatric patients weighing less than 60 kg, the administration volume for the recommended dose (0.75 mg/kg) is shown in Table 2; withdraw the appropriate volume from the vial.

Table 2: Injection Volumes of USTEKINUMAB-TTWE 45 mg/0.5 mL Vials for Pediatric Patients 6 Years of Age and Older with Plaque Psoriasis and Pediatric Patients 6 Years of Age and Older with Psoriatic Arthritis [Refer to 2.2 Psoriatic Arthritis; Subcutaneous Pediatric Dosage Regimen.] Weighing Less Than 60 kg
Body Weight (kg) at the time of dosing | Dose (mg) | Volume of injection (mL)
15 | 11.3 | 0.12
16 | 12 | 0.13
17 | 12.8 | 0.14
18 | 13.5 | 0.15
19 | 14.3 | 0.16
20 | 15 | 0.17
21 | 15.8 | 0.17
22 | 16.5 | 0.18
23 | 17.3 | 0.19
24 | 18 | 0.20
25 | 18.8 | 0.21
26 | 19.5 | 0.22
27 | 20.3 | 0.22
28 | 21 | 0.23
29 | 21.8 | 0.24
30 | 22.5 | 0.25
31 | 23.3 | 0.26
32 | 24 | 0.27
33 | 24.8 | 0.27
34 | 25.5 | 0.28
35 | 26.3 | 0.29
36 | 27 | 0.30
37 | 27.8 | 0.31
38 | 28.5 | 0.32
39 | 29.3 | 0.32
40 | 30 | 0.33
41 | 30.8 | 0.34
42 | 31.5 | 0.35
43 | 32.3 | 0.36
44 | 33 | 0.37
45 | 33.8 | 0.37
46 | 34.5 | 0.38
47 | 35.3 | 0.39
48 | 36 | 0.40
49 | 36.8 | 0.41
50 | 37.5 | 0.42
51 | 38.3 | 0.42
52 | 39 | 0.43
53 | 39.8 | 0.44
54 | 40.5 | 0.45
55 | 41.3 | 0.46
56 | 42 | 0.46
57 | 42.8 | 0.47
58 | 43.5 | 0.48
59 | 44.3 | 0.49

2.2 Recommended Dosage in Psoriatic Arthritis

Subcutaneous Adult Dosage Regimen

- The recommended dosage is 45 mg initially and 4 weeks later, followed by 45 mg every 12 weeks.
- For patients with co-existent moderate-to-severe plaque psoriasis weighing more than 100 kg, the recommended dosage is 90 mg initially and 4 weeks later, followed by 90 mg every 12 weeks.

Subcutaneous Pediatric Dosage Regimen

Administer USTEKINUMAB-TTWE subcutaneously at Weeks 0 and 4, then every 12 weeks thereafter.

The recommended dose of USTEKINUMAB-TTWE for pediatric patients 6 years of age and older with psoriatic arthritis, based on body weight, is shown below (Table 3).

Table 3: Recommended Dose of USTEKINUMAB-TTWE for Subcutaneous Injection in Pediatric Patients 6 Years of Age and Older with Psoriatic Arthritis
Body Weight of Patient at the Time of Dosing | Recommended Dose
less than 60 kg [For pediatric patients weighing less than 60 kg, the administration volume for the recommended dose (0.75 mg/kg) is shown in Table 2; withdraw the appropriate volume from the vial.] | 0.75 mg/kg
60 kg or more | 45 mg
greater than 100 kg with co-existent moderate-to-severe plaque psoriasis | 90 mg

2.3 Recommended Dosage in Crohn's Disease and Ulcerative Colitis

Intravenous Induction Adult Dosage Regimen

A single intravenous infusion dose of USTEKINUMAB-TTWE using the weight-based dosage regimen specified in Table 4 [see Dosage and Administration (2.5)].

Table 4: Initial Intravenous Dosage of USTEKINUMAB-TTWE
Body Weight of Patient at the time of dosing | Dose | Number of 130 mg/26 mL (5 mg/mL) USTEKINUMAB-TTWE vials
55 kg or less | 260 mg | 2
more than 55 kg to 85 kg | 390 mg | 3
more than 85 kg | 520 mg | 4

Subcutaneous Maintenance Adult Dosage Regimen

The recommended maintenance dosage is a subcutaneous 90 mg dose administered 8 weeks after the initial intravenous dose, then every 8 weeks thereafter.

2.4 General Considerations for Administration

- USTEKINUMAB-TTWE is intended for use under the guidance and supervision of a healthcare provider. USTEKINUMAB-TTWE should only be administered to patients who will be closely monitored and have regular follow-up visits with a healthcare provider. The appropriate dose should be determined by a healthcare provider using the patient's current weight at the time of dosing. In pediatric patients, it is recommended that USTEKINUMAB-TTWE be administered by a healthcare provider. If a healthcare provider determines that it is appropriate, a patient may self-inject or a caregiver may inject USTEKINUMAB-TTWE after proper training in subcutaneous injection technique. Instruct patients to follow the directions provided in the Instructions for Use [see Instructions for Use].
- It is recommended that each injection be administered at a different anatomic location (such as upper arms, gluteal regions, thighs, or any quadrant of abdomen) than the previous injection, and not into areas where the skin is tender, bruised, erythematous, or indurated. When using the vial, a 1 mL syringe with a 27 gauge, ½ inch needle is recommended.
- Prior to administration, visually inspect USTEKINUMAB-TTWE for particulate matter and discoloration. USTEKINUMAB-TTWE is a clear, colorless to light yellow, sterile and preservative-free solution. Do not use USTEKINUMAB-TTWE if it is discolored or cloudy, or if other particulate matter is present. USTEKINUMAB-TTWE does not contain preservatives; therefore, discard any unused product remaining in the vial and/or syringe.

2.5 Preparation and Administration of USTEKINUMAB-TTWE 130 mg/26 mL (5 mg/mL) Vial for Intravenous Infusion (Crohn's Disease and Ulcerative Colitis)

USTEKINUMAB-TTWE solution for intravenous infusion must be diluted, prepared and infused by a healthcare professional using aseptic technique.

1. Calculate the dose and the number of USTEKINUMAB-TTWE vials needed based on patient weight (Table 4). Each 26 mL vial of USTEKINUMAB-TTWE contains 130 mg of ustekinumab-ttwe.
2. Withdraw, and then discard a volume of the 0.9% Sodium Chloride Injection, USP from the 250 mL infusion bag equal to the volume of USTEKINUMAB-TTWE to be added (discard 26 mL sodium chloride for each vial of USTEKINUMAB-TTWE needed, for 2 vials- discard 52 mL, for 3 vials- discard 78 mL, 4 vials- discard 104 mL). Alternatively, a 250 mL infusion bag containing 0.45% Sodium Chloride Injection, USP may be used.
3. Withdraw 26 mL of USTEKINUMAB-TTWE from each vial needed and add it to the 250 mL infusion bag. The final volume in the infusion bag should be 250 mL. Gently mix. Protect from light.
4. Visually inspect the diluted solution before infusion. Do not use if visibly opaque particles, discoloration or foreign particles are observed.
5. Infuse the diluted solution over a period of at least one hour. Once diluted in the infusion bag, the infusion should be completely administered within 36 hours at room temperature up to 30°C (86°F) .
6. Use only an infusion set with an in-line, sterile, non-pyrogenic, low protein-binding filter (pore size 0.2 micrometer).
7. Do not infuse USTEKINUMAB-TTWE concomitantly in the same intravenous line with other agents.
8. USTEKINUMAB-TTWE does not contain preservatives. Each vial is for one-time use in only one patient. Discard any remaining solution. Dispose any unused medicinal product in accordance with local requirements.

Storage

- The diluted infusion solution may be kept at room temperature up to 30°C (86°F) for up to 36 hours including infusion period.
- If necessary, the diluted infusion solution may be stored refrigerated at 2°C to 8°C (36°F to 46°F) for up to 15 days. After removal from refrigeration, the diluted solution may be stored at room temperature at up to 30°C (86°F) for an additional 24 hours including infusion period. Storage time at refrigerated or room temperature begins once the diluted solution has been prepared. Do not freeze. Protect from light. Discard any unused portion of the infusion solution.

3 DOSAGE FORMS AND STRENGTHS

USTEKINUMAB-TTWE (ustekinumab-ttwe) is a clear, colorless to light yellow, sterile and preservative-free solution.

Subcutaneous Injection

- Injection: 45 mg/0.5 mL or 90 mg/mL solution in a single-dose prefilled syringe
- Injection: 45 mg/0.5 mL solution in a single-dose vial

Intravenous Infusion

- Injection: 130 mg/26 mL (5 mg/mL) solution in a single-dose vial

4 CONTRAINDICATIONS

USTEKINUMAB-TTWE is contraindicated in patients with clinically significant hypersensitivity to ustekinumab products or to any of the excipients in USTEKINUMAB-TTWE [see Warnings and Precautions (5.5)].

5 WARNINGS AND PRECAUTIONS

5.1 Infections

Ustekinumab products may increase the risk of infections and reactivation of latent infections. Serious bacterial, mycobacterial, fungal, and viral infections were observed in patients receiving ustekinumab products [see Adverse Reactions (6.1, 6.3)].

Serious infections requiring hospitalization, or otherwise clinically significant infections, reported in clinical trials included the following:

- Plaque Psoriasis: diverticulitis, cellulitis, pneumonia, appendicitis, cholecystitis, sepsis, osteomyelitis, viral infections, gastroenteritis and urinary tract infections.
- Psoriatic arthritis: cholecystitis.
- Crohn's disease: anal abscess, gastroenteritis, ophthalmic herpes zoster, pneumonia, and listeria meningitis.
- Ulcerative colitis: gastroenteritis, ophthalmic herpes zoster, pneumonia, and listeriosis.

Avoid initiating treatment with USTEKINUMAB-TTWE in patients with any clinically important active infection until the infection resolves or is adequately treated. Consider the risks and benefits of treatment prior to initiating use of USTEKINUMAB-TTWE in patients with a chronic infection or a history of recurrent infection.

Instruct patients to seek medical advice if signs or symptoms suggestive of an infection occur while on treatment with USTEKINUMAB-TTWE and discontinue USTEKINUMAB-TTWE for serious or clinically significant infections until the infection resolves or is adequately treated.

5.2 Theoretical Risk for Vulnerability to Particular Infections

Individuals genetically deficient in IL-12/IL-23 are particularly vulnerable to disseminated infections from mycobacteria (including nontuberculous, environmental mycobacteria), salmonella (including nontyphi strains), and Bacillus Calmette-Guerin (BCG) vaccinations. Serious infections and fatal outcomes have been reported in such patients.

It is not known whether patients with pharmacologic blockade of IL-12/IL-23 from treatment with ustekinumab products may be susceptible to these types of infections. Consider appropriate diagnostic testing (e.g., tissue culture, stool culture, as dictated by clinical circumstances).

5.3 Pre-treatment Evaluation for Tuberculosis

Evaluate patients for tuberculosis infection prior to initiating treatment with USTEKINUMAB-TTWE.

Avoid administering USTEKINUMAB-TTWE to patients with active tuberculosis infection. Initiate treatment of latent tuberculosis prior to administering USTEKINUMAB-TTWE. Consider anti-tuberculosis therapy prior to initiation of USTEKINUMAB-TTWE in patients with a past history of latent or active tuberculosis in whom an adequate course of treatment cannot be confirmed. Closely monitor patients receiving USTEKINUMAB-TTWE for signs and symptoms of active tuberculosis during and after treatment.

5.4 Malignancies

Ustekinumab products are immunosuppressants and may increase the risk of malignancy. Malignancies were reported among subjects who received ustekinumab in clinical trials [see Adverse Reactions (6.1)]. In rodent models, inhibition of IL-12/IL-23p40 increased the risk of malignancy [see Nonclinical Toxicology (13)].

The safety of ustekinumab products has not been evaluated in patients who have a history of malignancy or who have a known malignancy.

There have been post-marketing reports of the rapid appearance of multiple cutaneous squamous cell carcinomas in patients receiving ustekinumab products who had pre-existing risk factors for developing non-melanoma skin cancer. Monitor all patients receiving USTEKINUMAB-TTWE for the appearance of non-melanoma skin cancer. Closely follow patients greater than 60 years of age, those with a medical history of prolonged immunosuppressant therapy and those with a history of PUVA treatment [see Adverse Reactions (6.1)].

5.5 Serious Hypersensitivity Reactions

Serious hypersensitivity reactions, including anaphylaxis and angioedema, have been reported with ustekinumab products in clinical trials and postmarketing. Some serious hypersensitivity reactions have occurred during the first intravenous dose of ustekinumab products [see Adverse Reactions (6.1, 6.3)].

If a severe or clinically significant hypersensitivity reaction occurs, discontinue USTEKINUMAB-TTWE immediately and initiate appropriate medical treatment [see Contraindications (4)].

5.6 Posterior Reversible Encephalopathy Syndrome (PRES)

Two cases of posterior reversible encephalopathy syndrome (PRES), also known as Reversible Posterior Leukoencephalopathy Syndrome (RPLS), were reported in clinical trials. Cases have also been reported in postmarketing experience in patients with psoriasis, psoriatic arthritis and Crohn's disease. Clinical presentation included headaches, seizures, confusion, visual disturbances, and imaging changes consistent with PRES a few days to several months after ustekinumab product initiation. A few cases reported latency of a year or longer. Patients recovered with supportive care following withdrawal of ustekinumab products.

Monitor all patients treated with USTEKINUMAB-TTWE for signs and symptoms of PRES. If PRES is suspected, promptly administer appropriate treatment and discontinue USTEKINUMAB-TTWE.

5.7 Immunizations

Prior to initiating therapy with USTEKINUMAB-TTWE, patients should receive all age-appropriate immunizations as recommended by current immunization guidelines. Patients being treated with USTEKINUMAB-TTWE should avoid receiving live vaccines. Avoid administering BCG vaccines during treatment with USTEKINUMAB-TTWE or for one year prior to initiating treatment or one year following discontinuation of treatment. Caution is advised when administering live vaccines to household contacts of patients receiving USTEKINUMAB-TTWE because of the potential risk for shedding from the household contact and transmission to patient.

Non-live vaccinations received during a course of USTEKINUMAB-TTWE may not elicit an immune response sufficient to prevent disease.

5.8 Noninfectious Pneumonia

Cases of interstitial pneumonia, eosinophilic pneumonia and cryptogenic organizing pneumonia have been reported during post-approval use of ustekinumab products. Clinical presentations included cough, dyspnea, and interstitial infiltrates following one to three doses. Serious outcomes have included respiratory failure and prolonged hospitalization. Patients improved with discontinuation of therapy and in certain cases administration of corticosteroids. If diagnosis is confirmed, discontinue USTEKINUMAB-TTWE and institute appropriate treatment [see Adverse Reactions (6.3)].

6 ADVERSE REACTIONS

The following serious adverse reactions are discussed elsewhere in the label:

- Infections [see Warnings and Precautions (5.1)]
- Malignancies [see Warnings and Precautions (5.4)]
- Serious Hypersensitivity Reactions [see Warnings and Precautions (5.5)]
- Posterior Reversible Encephalopathy Syndrome (PRES) [see Warnings and Precautions (5.6)]
- Noninfectious Pneumonia [see Warnings and Precautions (5.8)]

6.1 Clinical Trials Experience

Because clinical trials are conducted under widely varying conditions, adverse reaction rates observed in the clinical trials of a drug cannot be directly compared to rates in the clinical trials of another drug and may not reflect the rates observed in practice.

Adult Subjects with Plaque Psoriasis

The safety data reflect exposure to ustekinumab in 3117 adult subjects with plaque psoriasis, including 2414 exposed for at least 6 months, 1855 exposed for at least one year, 1653 exposed for at least two years, 1569 exposed for at least three years, 1482 exposed for at least four years and 838 exposed for at least five years.

Table 5 summarizes the adverse reactions that occurred at a rate of at least 1% with higher rates in the ustekinumab groups during the placebo-controlled period of Ps STUDY 1 and Ps STUDY 2 [see Clinical Studies (14)].

Table 5: Adverse Reactions Reported by ≥1% of Subjects with Plaque Psoriasis and at Higher Rates in the Ustekinumab Groups through Week 12 in Ps STUDY 1 and Ps STUDY 2
 |  | Ustekinumab
 | Placebo | 45 mg | 90 mg
Subjects treated | 665 | 664 | 666
Nasopharyngitis | 51 (8%) | 56 (8%) | 49 (7%)
Upper respiratory tract infection | 30 (5%) | 36 (5%) | 28 (4%)
Headache | 23 (3%) | 33 (5%) | 32 (5%)
Fatigue | 14 (2%) | 18 (3%) | 17 (3%)
Back pain | 8 (1%) | 9 (1%) | 14 (2%)
Dizziness | 8 (1%) | 8 (1%) | 14 (2%)
Pharyngolaryngeal pain | 7 (1%) | 9 (1%) | 12 (2%)
Pruritus | 9 (1%) | 10 (2%) | 9 (1%)
Injection site erythema | 3 (<1%) | 6 (1%) | 13 (2%)
Myalgia | 4 (1%) | 7 (1%) | 8 (1%)
Depression | 3 (<1%) | 8 (1%) | 4 (1%)

Adverse reactions that occurred at rates less than 1% in the controlled period of Ps STUDIES 1 and 2 through week 12 included: cellulitis, herpes zoster, diverticulitis and certain injection site reactions (pain, swelling, pruritus, induration, hemorrhage, bruising, and irritation).

One case of PRES occurred during clinical trials in adult subjects with plaque psoriasis [see Warnings and Precautions (5.6)].

Infections

In the placebo-controlled period of clinical trials of subjects with plaque psoriasis (average follow-up of 12.6 weeks for subjects receiving placebo and 13.4 weeks for ustekinumab-treated subjects), 27% of ustekinumab-treated subjects reported infections (1.39 per patient-years of follow-up) compared with 24% of subjects receiving placebo (1.21 per patient-years of follow-up). Serious infections occurred in 0.3% of ustekinumab-treated subjects (0.01 per patient-years of follow-up) and in 0.4% of subjects receiving placebo (0.02 per patient-year of follow-up) [see Warnings and Precautions (5.1)].

In the controlled and non-controlled portions of clinical trials in subjects with plaque psoriasis (median follow-up of 3.2 years), representing 8998 patient-years of exposure, 72.3% of ustekinumab-treated subjects reported infections (0.87 per patient-years of follow-up). Serious infections were reported in 2.8% of subjects (0.01 per patient-years of follow-up).

Malignancies

In the controlled and non-controlled portions of clinical trials in subjects with plaque psoriasis (median follow-up of 3.2 years, representing 8998 patient-years of exposure), 1.7% of ustekinumab-treated subjects reported malignancies excluding non-melanoma skin cancers (0.60 per hundred patient-years of follow-up). Non-melanoma skin cancer was reported in 1.5% of ustekinumab-treated subjects (0.52 per hundred patient-years of follow-up) [see Warnings and Precautions (5.4)]. The most frequently observed malignancies other than non-melanoma skin cancer during the clinical trials were: prostate, melanoma, colorectal and breast. Malignancies other than non-melanoma skin cancer in ustekinumab-treated subjects during the controlled and uncontrolled portions of trials were similar in type and number to what would be expected in the general U.S. population according to the SEER database (adjusted for age, gender and race).^1

Pediatric Subjects with Plaque Psoriasis

The safety of ustekinumab was assessed in two trials of pediatric subjects with moderate to severe plaque psoriasis. Ps STUDY 3 evaluated safety for up to 60 weeks in 110 pediatric subjects 12 to 17 years old. Ps STUDY 4 evaluated safety for up to 56 weeks in 44 pediatric subjects 6 to 11 years old. The safety profile in pediatric subjects was similar to the safety profile from trials in adults with plaque psoriasis.

Psoriatic Arthritis

The safety of ustekinumab was assessed in 927 subjects in two randomized, double-blind, placebo-controlled trials in adults with active psoriatic arthritis (PsA). The overall safety profile of ustekinumab in subjects with PsA was consistent with the safety profile seen in clinical trials in adult subjects with plaque psoriasis. A higher incidence of arthralgia, nausea, and dental infections was observed in ustekinumab-treated subjects when compared with placebo- treated subjects (3% vs. 1% for arthralgia and 3% vs. 1% for nausea; 1% vs. 0.6% for dental infections) in the placebo-controlled portions of the PsA clinical trials.

Crohn's Disease

The safety of ustekinumab was assessed in 1407 subjects with moderately to severely active Crohn's disease (Crohn's Disease Activity Index [CDAI] greater than or equal to 220 and less than or equal to 450) in three randomized, double-blind, placebo-controlled, parallel-group, multicenter trials. These 1407 subjects included 40 subjects who received a prior investigational intravenous ustekinumab formulation but were not included in the efficacy analyses. In trials CD-1 and CD-2 there were 470 subjects who received ustekinumab 6 mg/kg as a weight-based single intravenous induction dose and 466 who received placebo [see Dosage and Administration (2.3)]. Subjects who were responders in either trial CD-1 or CD-2 were randomized to receive a subcutaneous maintenance regimen of either 90 mg ustekinumab every 8 weeks, or placebo for 44 weeks in trial CD-3. Subjects in these 3 trials may have received other concomitant therapies including aminosalicylates, immunomodulatory agents [azathioprine (AZA), 6- mercaptopurine (6-MP), methotrexate (MTX)], oral corticosteroids (prednisone or budesonide), and/or antibiotics for their Crohn's disease [see Clinical Studies (14.4)].

The overall safety profile of ustekinumab was consistent with the safety profile seen in the clinical trials in adult subjects with plaque psoriasis and psoriatic arthritis. Common adverse reactions in trials CD-1 and CD-2 and in trial CD-3 are listed in Table 6 and Table 7, respectively.

Table 6: Common Adverse Reactions Through Week 8 in Trials CD-1 and CD-2 occurring in ≥3% of Ustekinumab-Treated Subjects and Higher Than Subjects Receiving Placebo
 | Placebo N=466 | Ustekinumab 6 mg/kg single intravenous induction dose N=470
Vomiting | 3% | 4%

Other less common adverse reactions reported in subjects in trials CD-1 and CD-2 included asthenia (1% vs 0.4%), acne (1% vs 0.4%), and pruritus (2% vs 0.4%).

Table 7: Common Adverse Reactions Through Week 44 in Trial CD-3 Occurring in ≥3% of Ustekinumab-Treated Subjects and Higher Than Subjects Receiving Placebo
 | Placebo N=133 | Ustekinumab 90 mg subcutaneous maintenance dose every 8 weeks N=131
Nasopharyngitis | 8% | 11%
Injection site erythema | 0 | 5%
Vulvovaginal candidiasis/mycotic infection | 1% | 5%
Bronchitis | 3% | 5%
Pruritus | 2% | 4%
Urinary tract infection | 2% | 4%
Sinusitis | 2% | 3%

Infections

In subjects with Crohn's disease, serious or other clinically significant infections included anal abscess, gastroenteritis, and pneumonia. In addition, listeria meningitis and ophthalmic herpes zoster were reported in one subject each [see Warnings and Precautions (5.1)].

Malignancies

With up to one year of treatment in the Crohn's disease clinical trials, 0.2% of ustekinumab-treated subjects (0.36 events per hundred patient-years) and 0.2% of placebo-treated subjects (0.58 events per hundred patient-years) developed non- melanoma skin cancer. Malignancies other than non-melanoma skin cancers occurred in 0.2% of ustekinumab-treated subjects (0.27 events per hundred patient-years) and in none of the placebo-treated subjects.

Hypersensitivity Reactions Including Anaphylaxis

In CD trials, two subjects reported hypersensitivity reactions following ustekinumab administration. One subject experienced signs and symptoms consistent with anaphylaxis (tightness of the throat, shortness of breath, and flushing) after a single subcutaneous administration (0.1% of subjects receiving subcutaneous ustekinumab). In addition, one subject experienced signs and symptoms consistent with or related to a hypersensitivity reaction (chest discomfort, flushing, urticaria, and increased body temperature) after the initial intravenous ustekinumab dose (0.08% of subjects receiving intravenous ustekinumab). These subjects were treated with oral antihistamines or corticosteroids and in both cases symptoms resolved within an hour [see Warnings and Precautions (5.5)].

Ulcerative Colitis

The safety of ustekinumab was evaluated in two randomized, double-blind, placebo- controlled clinical trials (UC-1 [IV induction] and UC-2 [SC maintenance]) in 960 adult subjects with moderately to severely active ulcerative colitis [see Clinical Studies (14.5)]. The overall safety profile of ustekinumab in subjects with ulcerative colitis was consistent with the safety profile seen across all approved indications. Adverse reactions reported in at least 3% of ustekinumab-treated subjects and at a higher rate than placebo were:

- Induction (UC-1): nasopharyngitis (7% vs 4%).
- Maintenance (UC-2): nasopharyngitis (24% vs 20%), headache (10% vs 4%), abdominal pain (7% vs 3%), influenza (6% vs 5%), fever (5% vs. 4%), diarrhea (4% vs 1%), sinusitis (4% vs 1%), fatigue (4% vs 2%), and nausea (3% vs 2%).

Infections

In subjects with ulcerative colitis, serious or other clinically significant infections included gastroenteritis and pneumonia. In addition, listeriosis and ophthalmic herpes zoster were reported in one subject each [see Warnings and Precautions (5.1)].

Malignancies

With up to one year of treatment in the ulcerative colitis clinical trials, 0.4% of ustekinumab-treated subjects (0.48 events per hundred patient-years) and 0.0% of subjects receiving placebo (0.00 events per hundred patient-years) developed non- melanoma skin cancer. Malignancies other than non-melanoma skin cancers occurred in 0.5% of ustekinumab-treated subjects (0.64 events per hundred patient-years) and 0.2% of subjects receiving placebo (0.40 events per hundred patient-years).

6.2 Immunogenicity

The observed incidence of anti-drug antibodies is highly dependent on the sensitivity and specificity of the assay. Differences in assay methods preclude meaningful comparisons of the incidence of anti-drug antibodies in the studies described below with the incidence of anti-drug antibodies in other studies, including those of ustekinumab or of other ustekinumab products. Approximately 6 to 12.4% of subjects treated with ustekinumab in clinical trials in subjects with plaque psoriasis and psoriatic arthritis developed antibodies to ustekinumab, which were generally low-titer. In clinical trials in subjects with plaque psoriasis, antibodies to ustekinumab were associated with reduced or undetectable serum ustekinumab concentrations and reduced efficacy. In trials in subjects with plaque psoriasis, the majority of subjects who were positive for antibodies to ustekinumab had neutralizing antibodies.

In clinical trials in subjects with Crohn's disease and ulcerative colitis, 2.9% and 4.6% of subjects, respectively, developed antibodies to ustekinumab when treated with ustekinumab for approximately one year. No apparent association between the development of antibodies to ustekinumab and the development of injection site reactions was seen.

6.3 Postmarketing Experience

The following adverse reactions have been reported during post-approval use of ustekinumab products. Because these reactions are reported voluntarily from a population of uncertain size, it is not always possible to reliably estimate their frequency or establish a causal relationship to ustekinumab product exposure.

Immune system disorders: Hypersensitivity reactions (e.g., anaphylaxis, angioedema, dyspnea, rash, urticaria), including a fatal case that presented with chest tightness and dyspnea during infusion of the first dose.

Infections and infestations: Lower respiratory tract infection (including opportunistic fungal infections and tuberculosis).

Neurological disorders: Posterior Reversible Encephalopathy Syndrome (PRES).

Respiratory, thoracic and mediastinal disorders: Interstitial pneumonia, eosinophilic pneumonia and cryptogenic organizing pneumonia.

Skin reactions: Pustular psoriasis, erythrodermic psoriasis, hypersensitivity vasculitis.

7 DRUG INTERACTIONS

7.1 Concomitant Therapies

In trials in subjects with plaque psoriasis the safety of ustekinumab products in combination with immunosuppressive agents or phototherapy has not been evaluated. In trials in subjects with psoriatic arthritis, concomitant MTX use did not appear to influence the safety or efficacy of ustekinumab. In trials in subjects with Crohn's disease (CD-1 and CD-2) and ulcerative colitis (UC-1), immunomodulators (6-MP, AZA, MTX) were used concomitantly in approximately 30% of subjects and corticosteroids were used concomitantly in approximately 40% and 50% of Crohn's disease and ulcerative colitis subjects, respectively. Use of these concomitant therapies did not appear to influence the overall safety or efficacy of ustekinumab.

7.2 CYP450 Substrates

The formation of CYP450 enzymes can be suppressed by increased levels of certain cytokines (e.g., IL-1, IL-6, TNFα, IFN) during chronic inflammation. Thus, use of ustekinumab products, antagonists of IL-12 and IL-23, could normalize the formation of CYP450 enzymes. Upon initiation or discontinuation of USTEKINUMAB-TTWE in patients who are receiving concomitant CYP450 substrates, particularly those with a narrow therapeutic index, consider monitoring for therapeutic effect or drug concentration and adjust the individual dosage of the CYP substrate as needed. See the prescribing information of specific CYP substrates.

A CYP-mediated drug interaction effect was not observed in subjects with Crohn's disease [see Clinical Pharmacology (12.3)].

7.3 Allergen Immunotherapy

Ustekinumab products have not been evaluated in patients who have undergone allergy immunotherapy. Ustekinumab products may decrease the protective effect of allergen immunotherapy (decrease tolerance) which may increase the risk of an allergic reaction to a dose of allergen immunotherapy. Therefore, caution should be exercised in patients receiving or who have received allergen immunotherapy, particularly for anaphylaxis.

8 USE IN SPECIFIC POPULATIONS

8.1 Pregnancy

Risk Summary

Available data from the Organization of Teratology Information Specialists (OTIS)/MotherToBaby Pregnancy Registry, published literature and pharmacovigilance in pregnant women have not identified a ustekinumab-associated risk of major birth defects, miscarriage or other adverse maternal or fetal outcomes (see Data). There are risks to the mother and the fetus associated with inflammatory bowel disease (IBD) in pregnancy. In animal reproductive and developmental toxicity studies, no adverse developmental effects were observed in offspring after administration of ustekinumab to pregnant monkeys at exposures greater than 100 times the maximum recommended human dose (MRHD).

All pregnancies have a background risk of birth defect, loss, or other adverse outcomes. In the U.S. general population, the estimated background risk of major birth defects and miscarriage of clinically recognized pregnancies is 2% to 4% and 15% to 20%, respectively.

Clinical Considerations

Disease-associated Maternal and Embryo/Fetal Risk

Published data suggest that the risk of adverse pregnancy outcomes in women with IBD is associated with increased disease activity. Adverse pregnancy outcomes include preterm delivery (before 37 weeks of gestation), low birth weight (less than 2500 g) infants, and small for gestational age at birth.

Fetal/Neonatal Adverse Reactions

Transport of endogenous IgG antibodies across the placenta increases as pregnancy progresses, and peaks during the third trimester. Therefore, ustekinumab products may be present in infants exposed in utero. The potential clinical impact of ustekinumab product exposure in infants exposed in utero should be considered.

Data

Human Data

An observational pregnancy registry conducted by (OTIS)/MotherToBaby in the U.S. and Canada (enrollment between 2013 and 2019) assessed the risk of major birth defects, pattern of major and minor anomalies in live-born infants, miscarriage, and adverse infant outcomes in women with ustekinumab exposure. In the registry study, there were 101 participants and 107 pregnancies with exposure to ustekinumab (88 prospective; 19 retrospective). Most participants had a primary indication of CD (65.4%) or psoriasis (30.8%). The pregnancy registry did not identify a ustekinumab-associated risk of major birth defects, pattern of major or minor anomalies, increased risk of miscarriage or adverse infant outcomes. Methodological limitations of the registry include small sample size, lack of an internal comparison group, a mix of prospective and retrospective reports, and unmeasured confounders. The conclusions from the pregnancy registry were consistent with the published literature and pharmacovigilance.

Animal Data

Ustekinumab was tested in two embryo-fetal development toxicity studies in cynomolgus monkeys. No teratogenic or other adverse developmental effects were observed in fetuses from pregnant monkeys that were administered ustekinumab subcutaneously twice weekly or intravenously weekly during the period of organogenesis. Serum concentrations of ustekinumab in pregnant monkeys were greater than 100 times the serum concentration in patients treated subcutaneously with 90 mg of ustekinumab weekly for 4 weeks.

In a combined embryo-fetal development and pre- and post-natal development toxicity study, pregnant cynomolgus monkeys were administered subcutaneous doses of ustekinumab twice weekly at exposures greater than 100 times the MRHD from the beginning of organogenesis to Day 33 after delivery. Neonatal deaths occurred in the offspring of one monkey administered ustekinumab at 22.5 mg/kg and one monkey dosed at 45 mg/kg. No ustekinumab-related effects on functional, morphological, or immunological development were observed in the neonates from birth through six months of age.

8.2 Lactation

Risk Summary

Limited data from published literature suggests that ustekinumab is present in human breast milk. There are no available data on the effects of ustekinumab products on milk production. The effects of local gastrointestinal exposure and limited systemic exposure in the breastfed infant to ustekinumab products are unknown. No adverse effects on the breastfed infant causally related to ustekinumab products have been identified in the published literature or postmarketing experience.

The developmental and health benefits of breastfeeding should be considered along with the mother's clinical need for USTEKINUMAB-TTWE and any potential adverse effects on the breastfed child from USTEKINUMAB-TTWE or from the underlying maternal condition.

8.4 Pediatric Use

Plaque Psoriasis

The safety and effectiveness of USTEKINUMAB-TTWE have been established for the treatment of moderate to severe plaque psoriasis in pediatric patients 6 years of age and older who are candidates for phototherapy or systemic therapy.

Use of USTEKINUMAB-TTWE in pediatric patients 12 to less than 17 years of age is supported by evidence from a multicenter, randomized, 60 week trial (Ps STUDY 3) of ustekinumab that included a 12 week, double-blind, placebo-controlled, parallel group portion, in 110 pediatric subjects 12 years of age and older [see Adverse Reactions (6.1), Clinical Studies (14.2)].

Use of USTEKINUMAB-TTWE in pediatric patients 6 to 11 years of age is supported by evidence from an open- label, single-arm, efficacy, safety and pharmacokinetics trial (Ps STUDY 4) of ustekinumab in 44 subjects [see Adverse Reactions (6.1), Clinical Pharmacology (12.3)].

The safety and effectiveness of USTEKINUMAB-TTWE have not been established in pediatric patients less than 6 years of age with plaque psoriasis.

Psoriatic Arthritis

The safety and effectiveness of USTEKINUMAB-TTWE have been established for treatment of psoriatic arthritis in pediatric patients 6 years of age and older.

Use of USTEKINUMAB-TTWE in these age groups is supported by evidence from adequate and well controlled trials of ustekinumab in adult subjects with psoriasis and PsA, pharmacokinetic data from adult subjects with psoriasis, adult subjects with PsA and pediatric subjects with psoriasis, and safety data of ustekinumab from two clinical trials in 44 pediatric subjects 6 to 11 years old with psoriasis and 110 pediatric subjects 12 years of age and older with psoriasis. The observed pre-dose (trough) concentrations are generally comparable between adult subjects with psoriasis, adult subjects with PsA and pediatric subjects with psoriasis, and the PK exposure is expected to be comparable between adult and pediatric subjects with PsA [see Adverse Reactions (6.1), Clinical Pharmacology (12.3), and Clinical Studies (14.1, 14.2, 14.3)].

The safety and effectiveness of USTEKINUMAB-TTWE have not been established in pediatric patients less than 6 years old with psoriatic arthritis.

Crohn's Disease and Ulcerative Colitis

The safety and effectiveness of USTEKINUMAB-TTWE have not been established in pediatric patients with Crohn's disease or ulcerative colitis.

8.5 Geriatric Use

Of the 6709 subjects exposed to ustekinumab, a total of 340 were 65 years of age or older (183 subjects with plaque psoriasis, 65 subjects with psoriatic arthritis, 58 subjects with Crohn's disease and 34 subjects with ulcerative colitis), and 40 subjects were 75 years of age or older. Clinical trials of ustekinumab did not include sufficient numbers of subjects 65 years of age and older to determine whether they respond differently from younger adult subjects.

10 OVERDOSAGE

Single doses up to 6 mg/kg intravenously have been administered in clinical trials without dose-limiting toxicity. In case of overdosage, monitor the patient for any signs or symptoms of adverse reactions or effects and institute appropriate symptomatic treatment immediately. Consider contacting the Poison Help line 1-800-222-1222 or a medical toxicologist for additional overdose management recommendations.

11 DESCRIPTION

Ustekinumab-ttwe, a human IgG1κ monoclonal antibody, is a human interleukin-12 and -23 antagonist. Using DNA recombinant technology, ustekinumab-ttwe is produced in a Chinese hamster ovary cell line. The manufacturing process contains steps for the clearance of viruses. Ustekinumab-ttwe is comprised of 1326 amino acids and has an estimated molecular mass that ranges from 148,079 to 149,690 Daltons.

USTEKINUMAB-TTWE (ustekinumab-ttwe) injection is a clear, colorless to light yellow, sterile and preservative-free solution with pH of 5.7– 6.3.

USTEKINUMAB-TTWE for Subcutaneous Use

Available as 45 mg of ustekinumab-ttwe in 0.5 mL and 90 mg of ustekinumab-ttwe in 1 mL, supplied as a sterile solution in a single-dose prefilled syringe with a 29 gauge fixed ½ inch needle and as 45 mg of ustekinumab-ttwe in 0.5 mL in a single-dose Type I glass vial with a coated stopper. The syringe is fitted with a passive needle guard and a needle cover.

Each 0.5 mL prefilled syringe, or vial delivers 45 mg ustekinumab-ttwe, histidine (0.095 mg), histidine hydrochloride monohydrate (0.405 mg), polysorbate 80 (0.02 mg), and sucrose (42.5 mg).

Each 1 mL prefilled syringe delivers 90 mg ustekinumab-ttwe, histidine (0.19 mg), histidine hydrochloride monohydrate (0.81 mg), polysorbate 80 (0.04 mg), and sucrose (85 mg).

USTEKINUMAB-TTWE for Intravenous Infusion

Available as 130 mg of ustekinumab-ttwe in 26 mL, supplied as a single-dose Type I glass vial with a coated stopper.

Each 26 mL vial delivers 130 mg ustekinumab-ttwe, edetate disodium (0.52 mg), histidine (20 mg), histidine hydrochloride monohydrate (27 mg), methionine (10.4 mg), polysorbate 80 (10.4 mg) and sucrose (2,210 mg).

12 CLINICAL PHARMACOLOGY

12.1 Mechanism of Action

Ustekinumab products are human IgG1κ monoclonal antibodies that bind with specificity to the p40 protein subunit used by both the IL-12 and IL-23 cytokines. IL-12 and IL-23 are naturally occurring cytokines that are involved in inflammatory and immune responses, such as natural killer cell activation and CD4+ T-cell differentiation and activation. In in vitro models, ustekinumab products were shown to disrupt IL-12 and IL-23 mediated signaling and cytokine cascades by disrupting the interaction of these cytokines with a shared cell- surface receptor chain, IL-12Rβ1. The cytokines IL-12 and IL-23 have been implicated as important contributors to the chronic inflammation that is a hallmark of Crohn's disease and ulcerative colitis. In animal models of colitis, genetic absence or antibody blockade of the p40 subunit of IL-12 and IL-23, the target of ustekinumab products, was shown to be protective.

12.2 Pharmacodynamics

Plaque Psoriasis

In a small exploratory trial, a decrease was observed in the expression of mRNA of its molecular targets IL-12 and IL-23 in lesional skin biopsies measured at baseline and up to two weeks post-treatment in subjects with plaque psoriasis.

Ulcerative Colitis

In both trial UC-1 (induction) and trial UC-2 (maintenance), a positive relationship was observed between exposure and rates of clinical remission, clinical response, and endoscopic improvement. The response rate approached a plateau at the ustekinumab exposures associated with the recommended dosing regimen for maintenance treatment [see Clinical Studies (14.5)].

12.3 Pharmacokinetics

Absorption

In adult subjects with plaque psoriasis, the median time to reach the maximum serum concentration (Tmax) was 13.5 days and 7 days, respectively, after a single subcutaneous administration of 45 mg (N=22) and 90 mg (N=24) of ustekinumab. In healthy subjects (N=30), the median Tmax value (8.5 days) following a single subcutaneous administration of 90 mg of ustekinumab was comparable to that observed in subjects with plaque psoriasis.

Following multiple subcutaneous doses of ustekinumab in adult subjects with plaque psoriasis, steady-state serum concentrations of ustekinumab were achieved by Week 28. The mean (±SD) steady-state trough serum ustekinumab concentrations were 0.69 ± 0.69 mcg/mL for subjects less than or equal to 100 kg receiving a 45 mg dose and 0.74 ± 0.78 mcg/mL for subjects greater than 100 kg receiving a 90 mg dose. There was no apparent accumulation in serum ustekinumab concentration over time when given subcutaneously every 12 weeks.

Following the recommended intravenous induction dose, mean ±SD peak serum ustekinumab concentration was 125.2 ± 33.6 mcg/mL in subjects with Crohn's disease, and 129.1 ± 27.6 mcg/mL in subjects with ulcerative colitis. Starting at Week 8, the recommended subcutaneous maintenance dosing of 90 mg ustekinumab was administered every 8 weeks. Steady state ustekinumab concentration was achieved by the start of the second maintenance dose. There was no apparent accumulation in ustekinumab concentration over time when given subcutaneously every 8 weeks. Mean ± SD steady-state trough concentration was 2.5 ± 2.1 mcg/mL in subjects with Crohn's disease, and 3.3 ± 2.3 mcg/mL in subjects with ulcerative colitis for 90 mg ustekinumab administered every 8 weeks.

Distribution

Population pharmacokinetic analyses showed that the volume of distribution of ustekinumab in the central compartment was 2.7 L (95% CI: 2.69, 2.78) in subjects with Crohn's disease and 3.0 L (95% CI: 2.96, 3.07) in subjects with ulcerative colitis. The total volume of distribution at steady-state was 4.6 L in subjects with Crohn's disease and 4.4 L in subjects with ulcerative colitis.

Elimination

The mean (±SD) half-life ranged from 14.9 ± 4.6 to 45.6 ± 80.2 days across all trials in subjects with plaque psoriasis following subcutaneous administration. Population pharmacokinetic analyses showed that the clearance of ustekinumab was 0.19 L/day (95% CI: 0.185, 0.197) in subjects with Crohn's disease and 0.19 L/day (95% CI: 0.179, 0.192) in subjects with ulcerative colitis with an estimated median terminal half-life of approximately 19 days for both IBD (Crohn's disease and ulcerative colitis) populations.

These results indicate the pharmacokinetics of ustekinumab were similar between subjects with Crohn's disease and ulcerative colitis.

Metabolism

The metabolic pathway of ustekinumab products has not been characterized. As a human IgG1κ monoclonal antibody, ustekinumab products are expected to be degraded into small peptides and amino acids via catabolic pathways in the same manner as endogenous IgG.

Specific Populations

Weight

When given the same dose, subjects with plaque psoriasis or psoriatic arthritis weighing more than 100 kg had lower median serum ustekinumab concentrations compared with those subjects weighing 100 kg or less. The median trough serum concentrations of ustekinumab in subjects of higher weight (greater than 100 kg) in the 90 mg group were comparable to those in subjects of lower weight (100 kg or less) in the 45 mg group.

Age: Geriatric Population

A population pharmacokinetic analysis (N=106/1937 subjects with plaque psoriasis greater than or equal to 65 years old) was performed to evaluate the effect of age on the pharmacokinetics of ustekinumab. There were no apparent changes in pharmacokinetic parameters (clearance and volume of distribution) in subjects older than 65 years old.

Age: Pediatric Population

Following multiple recommended doses of ustekinumab in pediatric subjects 6 years of age and older with plaque psoriasis, steady-state serum concentrations of ustekinumab were achieved by Week 28. At Week 28, the mean ±SD steady-state trough serum ustekinumab concentrations were 0.36 ± 0.26 mcg/mL and 0.54 ± 0.43 mcg/mL, respectively, in pediatric subjects 6 to 11 years of age and pediatric subjects 12 years of age and older.

Overall, the observed steady-state ustekinumab trough concentrations in pediatric subjects with plaque psoriasis were within the range of those observed for adult subjects with plaque psoriasis and adult subjects with PsA after administration of ustekinumab.

Drug Interaction Studies

The effects of IL-12 or IL-23 on the regulation of CYP450 enzymes were evaluated in an in vitro study using human hepatocytes, which showed that IL-12 and/or IL-23 at levels of 10 ng/mL did not alter human CYP450 enzyme activities (CYP1A2, 2B6, 2C9, 2C19, 2D6, or 3A4).

No clinically significant changes in exposure of caffeine (CYP1A2 substrate), warfarin (CYP2C9 substrate), omeprazole (CYP2C19 substrate), dextromethorphan (CYP2D6 substrate), or midazolam (CYP3A substrate) were observed when used concomitantly with ustekinumab at the approved recommended dosage in subjects with Crohn's disease [see Drug Interactions (7.2)].

Population pharmacokinetic analyses indicated that the clearance of ustekinumab was not impacted by concomitant MTX, NSAIDs, and oral corticosteroids, or prior exposure to a TNF blocker in subjects with psoriatic arthritis.

In subjects with Crohn's disease and ulcerative colitis, population pharmacokinetic analyses did not indicate changes in ustekinumab clearance with concomitant use of corticosteroids or immunomodulators (AZA, 6-MP, or MTX); and serum ustekinumab concentrations were not impacted by concomitant use of these medications.

13 NONCLINICAL TOXICOLOGY

13.1 Carcinogenesis, Mutagenesis, Impairment of Fertility

Animal studies have not been conducted to evaluate the carcinogenic or mutagenic potential of ustekinumab products. Published literature showed that administration of murine IL-12 caused an anti-tumor effect in mice that contained transplanted tumors and IL-12/IL- 23p40 knockout mice or mice treated with anti-IL-12/IL-23p40 antibody had decreased host defense to tumors. Mice genetically manipulated to be deficient in both IL-12 and IL- 23 or IL-12 alone developed UV-induced skin cancers earlier and more frequently compared to wild-type mice. The relevance of these experimental findings in mouse models for malignancy risk in humans is unknown.

No effects on fertility were observed in male cynomolgus monkeys that were administered ustekinumab at subcutaneous doses up to 45 mg/kg twice weekly (45 times the MRHD on a mg/kg basis) prior to and during the mating period. However, fertility and pregnancy outcomes were not evaluated in mated females.

No effects on fertility were observed in female mice that were administered an analogous IL-12/IL-23p40 antibody by subcutaneous administration at doses up to 50 mg/kg, twice weekly, prior to and during early pregnancy.

13.2 Animal Toxicology and/or Pharmacology

In a 26-week toxicology study, one out of 10 monkeys subcutaneously administered 45 mg/kg ustekinumab twice weekly for 26 weeks had a bacterial infection.

14 CLINICAL STUDIES

14.1 Adult Subjects with Plaque Psoriasis

Two multicenter, randomized, double-blind, placebo-controlled trials (Ps STUDY 1 and Ps STUDY 2) enrolled a total of 1996 subjects 18 years of age and older with plaque psoriasis who had a minimum body surface area involvement of 10%, and Psoriasis Area and Severity Index (PASI) score ≥12, and who were candidates for phototherapy or systemic therapy. Subjects with guttate, erythrodermic, or pustular psoriasis were excluded from the trials.

Ps STUDY 1 enrolled 766 subjects and Ps STUDY 2 enrolled 1230 subjects. The trials had the same design through Week 28. In both trials, subjects were randomized in equal proportion to placebo, 45 mg or 90 mg of ustekinumab. Subjects randomized to ustekinumab received 45 mg or 90 mg doses, regardless of weight, at Weeks 0, 4, and 16. Subjects randomized to receive placebo at Weeks 0 and 4 crossed over to receive ustekinumab (either 45 mg or 90 mg) at Weeks 12 and 16.

In both trials, subjects in all treatment groups had a median baseline PASI score ranging from approximately 17 to 18. Baseline PGA score was marked or severe in 44% of subjects in Ps STUDY 1 and 40% of subjects in Ps STUDY 2. Approximately two-thirds of all subjects had received prior phototherapy, 69% had received either prior conventional systemic or biologic therapy for the treatment of psoriasis, with 56% receiving prior conventional systemic therapy and 43% receiving prior biologic therapy. A total of 28% of subjects had a history of psoriatic arthritis.

In both trials, the endpoints were the proportion of subjects who achieved at least a 75% reduction in PASI score (PASI 75) from baseline to Week 12 and treatment success (cleared or minimal) on the Physician's Global Assessment (PGA). The PGA is a 6- category scale ranging from 0 (cleared) to 5 (severe) that indicates the physician's overall assessment of psoriasis focusing on plaque thickness/induration, erythema, and scaling.

Clinical Response

The results of Ps STUDY 1 and Ps STUDY 2 are presented in Table 8 below.

Table 8: Clinical Outcomes at Week 12 in Adult Subjects with Plaque Psoriasis in Ps STUDY 1 and Ps STUDY 2
 | Ps STUDY 1 |  |  | Ps STUDY 2
 |  | Ustekinumab |  |  | Ustekinumab
 | Placebo | 45 mg | 90 mg | Placebo | 45 mg | 90 mg
Subjects randomized | 255 | 255 | 256 | 410 | 409 | 411
PASI 75 response | 8 (3%) | 171 (67%) | 170 (66%) | 15 (4%) | 273 (67%) | 311 (76%)
PGA of Cleared or Minimal | 10 (4%) | 151 (59%) | 156 (61%) | 18 (4%) | 277 (68%) | 300 (73%)

Examination of age, gender, and race subgroups did not identify differences in response to ustekinumab among these subgroups.

In subjects who weighed 100 kg or less, response rates were comparable with both the 45 mg and 90 mg doses; however, in subjects who weighed greater than 100 kg, higher response rates were seen with 90 mg dosing compared with 45 mg dosing (Table 9 below).

Table 9: Clinical Outcomes by Weight at Week 12 in Adult Subjects with Plaque Psoriasis in Ps STUDY 1 and Ps STUDY 2
 | Ps STUDY 1 |  |  | Ps STUDY 2
 |  | Ustekinumab |  |  | Ustekinumab
 | Placebo | 45 mg | 90 mg | Placebo | 45 mg | 90 mg
Subjects randomized | 255 | 255 | 256 | 410 | 409 | 411
PASI 75 response [Subjects were dosed with trial medication at Weeks 0 and 4.]
≤100 kg | 4% | 74% | 65% | 4% | 73% | 78%
 | 6/166 | 124/168 | 107/164 | 12/290 | 218/297 | 225/289
>100 kg | 2% | 54% | 68% | 3% | 49% | 71%
 | 2/89 | 47/87 | 63/92 | 3/120 | 55/112 | 86/121
PGA of Cleared or Minimal
≤100 kg | 4% | 64% | 63% | 5% | 74% | 75%
 | 7/166 | 108/168 | 103/164 | 14/290 | 220/297 | 216/289
>100 kg | 3% | 49% | 58% | 3% | 51% | 69%
 | 3/89 | 43/87 | 53/92 | 4/120 | 57/112 | 84/121

Subjects in Ps STUDY 1 who were PASI 75 responders at both Weeks 28 and 40 were re-randomized at Week 40 to either continued dosing of ustekinumab (ustekinumab at Week 40) or to withdrawal of therapy (placebo at Week 40). At Week 52, 89% (144/162) of subjects re-randomized to ustekinumab treatment were PASI 75 responders compared with 63% (100/159) of subjects re-randomized to placebo (treatment withdrawal after Week 28 dose). The median time to loss of PASI 75 response among the subjects randomized to treatment withdrawal was 16 weeks.

14.2 Pediatric Subjects with Plaque Psoriasis

A multicenter, randomized, double blind, placebo-controlled trial (Ps STUDY 3) enrolled 110 pediatric subjects 12 years of age and older with a minimum BSA involvement of 10%, a PASI score greater than or equal to 12, and a PGA score greater than or equal to 3, who were candidates for phototherapy or systemic therapy and whose disease was inadequately controlled by topical therapy.

Subjects were randomized to receive placebo (n = 37), the recommended dose of ustekinumab (n = 36), or one-half the recommended dose of ustekinumab (n = 37) by subcutaneous injection at Weeks 0 and 4 followed by dosing every 12 weeks (q12w). The recommended dose of ustekinumab was 0.75 mg/kg for subjects weighing less than 60 kg, 45 mg for subjects weighing 60 kg to 100 kg, and 90 mg for subjects weighing greater than 100 kg. At Week 12, subjects who received placebo were crossed over to receive ustekinumab at the recommended dose or one-half the recommended dose.

Of the pediatric subjects, approximately 63% had prior exposure to phototherapy or conventional systemic therapy and approximately 11% had prior exposure to biologics.

The endpoints were the proportion of subjects who achieved a PGA score of cleared (0) or minimal (1), PASI 75, and PASI 90 at Week 12. Subjects were followed for up to 60 weeks following first administration of trial agent.

Clinical Response

The efficacy results at Week 12 for Ps STUDY 3 are presented in Table 10.

Table 10: Efficacy Results at Week 12 in Pediatric Subjects 12 Years of Age and Older with Plaque Psoriasis in Ps STUDY 3
 | Ps STUDY 3
 | Placebo n (%) | Ustekinumab [Using the weight-based dosage regimen specified in Table 1 and Table 2.] n (%)
N | 37 | 36
PGA
PGA of cleared (0) or minimal (1) | 2 (5.4%) | 25 (69.4%)
PASI
PASI 75 responders | 4 (10.8%) | 29 (80.6%)
PASI 90 responders | 2 (5.4%) | 22 (61.1%)

14.3 Psoriatic Arthritis

The safety and efficacy of ustekinumab was assessed in 927 subjects (PsA STUDY 1, n=615; PsA STUDY 2, n=312), in two randomized, double-blind, placebo-controlled trials in adult subjects 18 years of age and older with active PsA (≥5 swollen joints and ≥5 tender joints) despite nonsteroidal anti-inflammatory (NSAID) or disease modifying antirheumatic (DMARD) therapy. Subjects in these trials had a diagnosis of PsA for at least 6 months. Subjects with each subtype of PsA were enrolled, including polyarticular arthritis with the absence of rheumatoid nodules (39%), spondylitis with peripheral arthritis (28%), asymmetric peripheral arthritis (21%), distal interphalangeal involvement (12%) and arthritis mutilans (0.5%). Over 70% and 40% of the subjects, respectively, had enthesitis and dactylitis at baseline.

Subjects were randomized to receive treatment with ustekinumab 45 mg, 90 mg, or placebo subcutaneously at Weeks 0 and 4 followed by every 12 weeks (q12w) dosing. Approximately 50% of subjects continued on stable doses of MTX (≤25 mg/week). The primary endpoint was the percentage of subjects achieving ACR 20 response at Week 24.

In PsA STUDY 1 and PsA STUDY 2, 80% and 86% of the subjects, respectively, had been previously treated with DMARDs. In PsA STUDY 1, previous treatment with anti-tumor necrosis factor (TNF)-α agent was not allowed. In PsA STUDY 2, 58% (n=180) of the subjects had been previously treated with TNF blocker, of whom over 70% had discontinued their TNF blocker treatment for lack of efficacy or intolerance at any time.

Clinical Response

In both trials, a greater proportion of subjects achieved ACR 20, ACR 50 and PASI 75 response in the ustekinumab 45 mg and 90 mg groups compared to placebo at Week 24 (see Table 11). ACR 70 responses were also higher in the ustekinumab 45 mg and 90 mg groups, although the difference was only numerical (p=NS) in STUDY 2. Responses were consistent in subjects treated with ustekinumab alone or in combination with methotrexate. Responses were similar in subjects regardless of prior TNFα exposure.

Table 11: ACR 20, ACR 50, ACR 70 and PASI 75 responses in PsA STUDY 1 and PsA STUDY 2 at Week 24
 | PsA STUDY 1 |  |  | PsA STUDY 2
 |  | Ustekinumab |  |  | Ustekinumab
 | Placebo | 45 mg | 90 mg | Placebo | 45 mg | 90 mg
Number of subjects Randomized | 206 | 205 | 204 | 104 | 103 | 105
ACR 20 response, N (%) | 47 (23%) | 87 (42%) | 101 (50%) | 21 (20%) | 45 (44%) | 46 (44%)
ACR 50 response, N (%) | 18 (9%) | 51 (25%) | 57 (28%) | 7 (7%) | 18 (17%) | 24 (23%)
ACR 70 response, N (%) | 5 (2%) | 25 (12%) | 29 (14%) | 3 (3%) | 7 (7%) | 9 (9%)
Number of subjects with ≥ 3% BSA [Number of subjects with ≥ 3% BSA psoriasis skin involvement at baseline] | 146 | 145 | 149 | 80 | 80 | 81
PASI 75 response, N (%) | 16 (11%) | 83 (57%) | 93 (62%) | 4 (5%) | 41 (51%) | 45 (56%)

The percent of subjects achieving ACR 20 responses by visit is shown in Figure 1.

Figure 1: Percent of subjects achieving ACR 20 response through Week 24

The results of the components of the ACR response criteria are shown in Table 12.

Table 12: Mean change from baseline in ACR components at Week 24
 | PsA STUDY 1
 |  | Ustekinumab
 | Placebo (N = 206) | 45 mg (N = 205) | 90 mg (N = 204)
Number of swollen joints [Number of swollen joints counted (0–66)]
Baseline | 15 | 12 | 13
Mean Change at Week 24 | -3 | -5 | -6
Number of tender joints [Number of tender joints counted (0–68)]
Baseline | 25 | 22 | 23
Mean Change at Week 24 | -4 | -8 | -9
Subject's assessment of pain [Visual analogue scale; 0= best, 10=worst.]
Baseline | 6.1 | 6.2 | 6.6
Mean Change at Week 24 | -0.5 | -2.0 | -2.6
Subject global assessment
Baseline | 6.1 | 6.3 | 6.4
Mean Change at Week 24 | -0.5 | -2.0 | -2.5
Physician global assessment
Baseline | 5.8 | 5.7 | 6.1
Mean Change at Week 24 | -1.4 | -2.6 | -3.1
Disability index (HAQ) [Disability Index of the Health Assessment Questionnaire; 0 = best, 3 = worst, measures the patient's ability to perform the following: dress/groom, arise, eat, walk, reach, grip, maintain hygiene, and maintain daily activity.]
Baseline | 1.2 | 1.2 | 1.2
Mean Change at Week 24 | -0.1 | -0.3 | -0.4
CRP (mg/dL) [CRP: (Normal Range 0.0–1.0 mg/dL)]
Baseline | 1.6 | 1.7 | 1.8
Mean Change at Week 24 | 0.01 | -0.5 | -0.8

An improvement in enthesitis and dactylitis scores was observed in each ustekinumab group compared with placebo at Week 24.

Physical Function

Ustekinumab-treated subjects showed improvement in physical function compared to subjects receiving placebo as assessed by HAQ-DI at Week 24. In both trials, the proportion of HAQ-DI responders (≥0.3 improvement in HAQ-DI score) was greater in the ustekinumab 45 mg and 90 mg groups compared to placebo at Week 24.

14.4 Crohn's Disease

Ustekinumab was evaluated in three randomized, double-blind, placebo-controlled clinical trials in adult subjects with moderately to severely active Crohn's disease (Crohn's Disease Activity Index [CDAI] score of 220 to 450). There were two 8-week intravenous induction trials (CD-1 and CD-2) followed by a 44-week subcutaneous randomized withdrawal maintenance trial (CD-3) representing 52 weeks of therapy. Subjects in CD- 1 had failed or were intolerant to treatment with one or more TNF blockers, while subjects in CD-2 had failed or were intolerant to treatment with immunomodulators or corticosteroids, but never failed treatment with a TNF blocker.

Trials CD-1 and CD-2

In trials CD-1 and CD-2, 1409 subjects were randomized, of whom 1368 (CD-1, n=741; CD-2, n=627) were included in the final efficacy analysis. Induction of clinical response (defined as a reduction in CDAI score of greater than or equal to 100 points or CDAI score of less than 150) at Week 6 and clinical remission (defined as a CDAI score of less than 150) at Week 8 were evaluated. In both trials, subjects were randomized to receive a single intravenous administration of ustekinumab at either approximately 6 mg/kg, placebo (see Table 4), or 130 mg (a lower dose than recommended).

In trial CD-1, subjects had failed or were intolerant to prior treatment with a TNF blocker: 29% subjects had an inadequate initial response (primary non-responders), 69% responded but subsequently lost response (secondary non-responders) and 36% were intolerant to a TNF blocker. Of these subjects, 48% failed or were intolerant to one TNF blocker and 52% had failed 2 or 3 prior TNF blockers. At baseline and throughout the trial, approximately 46% of the subjects were receiving corticosteroids and 31% of the subjects were receiving immunomodulators (AZA, 6-MP, MTX). The median baseline CDAI score was 319 in the ustekinumab approximately 6 mg/kg group and 313 in the placebo group.

In trial CD-2, subjects had failed or were intolerant to prior treatment with corticosteroids (81% of subjects), at least one immunomodulator (6-MP, AZA, MTX; 68% of subjects), or both (49% of subjects). Additionally, 69% never received a TNF blocker and 31% previously received but had not failed a TNF blocker. At baseline, and throughout the trial, approximately 39% of the subjects were receiving corticosteroids and 35% of the subjects were receiving immunomodulators (AZA, 6-MP, MTX). The median baseline CDAI score was 286 in the ustekinumab and 290 in the placebo group.

In these induction trials, a greater proportion of subjects treated with ustekinumab (at the recommended dose of approximately 6 mg/kg dose) achieved clinical response at Week 6 and clinical remission at Week 8 compared to placebo (see Table 13 for clinical response and remission rates). Clinical response and remission were significant as early as Week 3 in ustekinumab-treated subjects and continued to improve through Week 8.

Table 13: Induction of Clinical Response and Remission in CD-1 [Patient population consisted of subjects who failed or were intolerant to TNF blocker therapy] and CD-2 [Patient population consisted of subjects who failed or were intolerant to corticosteroids or immunomodulators (e.g., 6-MP, AZA, MTX) and previously received but not failed a TNF blocker or were never treated with a TNF blocker.]
 | CD-1 n = 741 |  |  | CD-2 n = 627
 | Placebo N = 247 | Ustekinumab [Infusion dose of ustekinumab using the weight-based dosage regimen specified in Table 4.] N = 249 | Treatment difference and 95% Cl | Placebo N = 209 | Ustekinumab N = 209 | Treatment difference and 95% Cl
Clinical Response (100 point), Week 6 | 53 (21%) | 84 (34%) [0.001≤ p < 0.01] | 12% (4%, 20%) | 60 (29%) | 116 (56%) [p < 0.001] | 27% (18%, 36%)
Clinical Remission, Week 8 | 18 (7%) | 52 (21%) | 14% (8%, 20%) | 41 (20%) | 84 (40%) | 21% (12%, 29%)
Clinical Response (100 point), Week 8 | 50 (20%) | 94 (38%) | 18% (10%, 25%) | 67 (32%) | 121 (58%) | 26% (17%, 35%)
70 Point Response, Week 6 | 75 (30%) | 109 (44%) | 13% (5%, 22%) | 81 (39%) | 135 (65%) | 26% (17%, 35%)
70 Point Response, Week 3 | 67 (27%) | 101 (41%) | 13% (5%, 22%) | 66 (32%) | 106 (51%) | 19% (10%, 28%)
Clinical remission is defined as CDAI score < 150; Clinical response is defined as reduction in CDAI score by at least 100 points or being in clinical remission: 70 point response is defined as reduction in CDAI score by at least 70 points

Trial CD-3

The maintenance trial (CD-3), evaluated 388 subjects who achieved clinical response (≥ 100 point reduction in CDAI score) at Week 8 with either induction dose of ustekinumab in trials CD-1 or CD-2. Subjects were randomized to receive a subcutaneous maintenance regimen of either 90 mg ustekinumab every 8 weeks or placebo for 44 weeks (see Table 14).

Table 14: Clinical Response and Remission in CD-3 (Week 44; 52 weeks from initiation of the induction dose)
 | Placebo [The placebo group consisted of subjects who were in response to ustekinumab and were randomized to receive placebo at the start of maintenance therapy.] N = 131 [Subjects who achieved clinical response to ustekinumab at the end of the induction trial.] | 90 mg ustekinumab every 8 weeks N = 128 | Treatment difference and 95% CI
Clinical Remission | 47 (36%) | 68 (53%) [p < 0.01] | 17% (5%, 29%)
Clinical Response | 58 (44%) | 76 (59%) [0.01≤ p < 0.05] | 15% (3%, 27%)
Clinical Remission in subjects in remission at the start of maintenance therapy [Subjects in remission at the end of maintenance therapy who were in remission at the start of maintenance therapy. This does not account for any other time point during maintenance therapy.] | 36/79 (46%) | 52/78 (67%) | 21% (6%, 36%)
Clinical remission is defined as CDAI score < 150; Clinical response is defined as reduction in CDAI of at least 100 points or being in clinical remission

At Week 44, 47% of subjects who received ustekinumab were corticosteroid-free and in clinical remission, compared to 30% of subjects in the placebo group.

At Week 0 of trial CD-3, 34/56 (61%) ustekinumab-treated subjects who previously failed or were intolerant to TNF blocker therapies were in clinical remission and 23/56 (41%) of these subjects were in clinical remission at Week 44. In the placebo arm, 27/61 (44%) subjects were in clinical remission at Week 0 while 16/61 (26%) of these subjects were in remission at Week 44.

At Week 0 of trial CD-3, 46/72 (64%) ustekinumab-treated subjects who had previously failed immunomodulator therapy or corticosteroids (but not TNF blockers) were in clinical remission and 45/72 (63%) of these subjects were in clinical remission at Week 44. In the placebo arm, 50/70 (71%) of these subjects were in clinical remission at Week 0 while 31/70 (44%) were in remission at Week 44. In the subset of these subjects who were also naïve to TNF blockers, 34/52 (65%) of ustekinumab-treated subjects were in clinical remission at Week 44 as compared to 25/51 (49%) in the placebo arm.

Subjects who were not in clinical response 8 weeks after ustekinumab induction were not included in the primary efficacy analyses for trial CD-3; however, these subjects were eligible to receive a 90 mg subcutaneous injection of ustekinumab upon entry into trial CD-3. Of these subjects, 102/219 (47%) achieved clinical response eight weeks later and were followed for the duration of the trial.

14.5 Ulcerative Colitis

Ustekinumab was evaluated in two randomized, double-blind, placebo-controlled clinical trials [UC-1 and UC-2 (NCT02407236)] in adult subjects with moderately to severely active ulcerative colitis who had an inadequate response to or failed to tolerate a biologic (i.e., TNF blocker and/or vedolizumab), corticosteroids, and/or 6-MP or AZA therapy. The 8-week intravenous induction trial (UC-1) was followed by the 44-week subcutaneous randomized withdrawal maintenance trial (UC-2) for a total of 52 weeks of therapy.

Disease assessment was based on the Mayo score, which ranged from 0 to 12 and has four subscores that were each scored from 0 (normal) to 3 (most severe): stool frequency, rectal bleeding, findings on centrally-reviewed endoscopy, and physician global assessment. Moderately to severely active ulcerative colitis was defined at baseline (Week 0) as Mayo score of 6 to 12, including a Mayo endoscopy subscore ≥2. An endoscopy score of 2 was defined by marked erythema, absent vascular pattern, friability, erosions; and a score of 3 was defined by spontaneous bleeding, ulceration. At baseline, subjects had a median Mayo score of 9, with 84% of subjects having moderate disease (Mayo score 6–10) and 15% having severe disease (Mayo score 11–12).

Subjects in these trials may have received other concomitant therapies including aminosalicylates, immunomodulatory agents (AZA, 6-MP, or MTX), and oral corticosteroids (prednisone).

Trial UC-1

In UC-1, 961 subjects were randomized at Week 0 to a single intravenous administration of ustekinumab of approximately 6 mg/kg, 130 mg (a lower dose than recommended), or placebo. Subjects enrolled in UC-1 had to have failed therapy with corticosteroids, immunomodulators or at least one biologic. A total of 51% had failed at least one biologic and 17% had failed both a TNF blocker and an integrin receptor blocker. Of the total population, 46% had failed corticosteroids or immunomodulators but were biologic-naïve and an additional 3% had previously received but had not failed a biologic. At induction baseline and throughout the trial, approximately 52% subjects were receiving oral corticosteroids, 28% subjects were receiving immunomodulators (AZA, 6-MP, or MTX) and 69% subjects were receiving aminosalicylates.

The primary endpoint was clinical remission at Week 8. Clinical remission with a definition of: Mayo stool frequency subscore of 0 or 1, Mayo rectal bleeding subscore of 0 (no rectal bleeding), and Mayo endoscopy subscore of 0 or 1 (Mayo endoscopy subscore of 0 defined as normal or inactive disease and Mayo subscore of 1 defined as presence of erythema, decreased vascular pattern and no friability) is provided in Table 15.

The secondary endpoints were clinical response, endoscopic improvement, and histologic-endoscopic mucosal improvement. Clinical response with a definition of (≥ 2 points and ≥ 30% decrease in modified Mayo score, defined as 3-component Mayo score without the Physician's Global Assessment, with either a decrease from baseline in the rectal bleeding subscore ≥1 or a rectal bleeding subscore of 0 or 1), endoscopic improvement with a definition of Mayo endoscopy subscore of 0 or 1, and histologic- endoscopic mucosal improvement with a definition of combined endoscopic improvement and histologic improvement of the colon tissue [neutrophil infiltration in <5% of crypts, no crypt destruction, and no erosions, ulcerations, or granulation tissue]) are provided in Table 15.

In UC-1, a significantly greater proportion of subjects treated with ustekinumab (at the recommended dose of approximately 6 mg/kg dose) were in clinical remission and response and achieved endoscopic improvement and histologic-endoscopic mucosal improvement compared to placebo (see Table 15).

Table 15: Proportion of Subjects Meeting Efficacy Endpoints at Week 8 in UC-1
Endpoint | Placebo N = 319 |  | Ustekinumab [Infusion dose of ustekinumab using the weight-based dosage regimen specified in Table 4.] N = 322 |  | Treatment difference and 97.5% CI [Adjusted treatment difference (97.5% CI)]
Endpoint | N | % | N | % | Treatment difference and 97.5% CI [Adjusted treatment difference (97.5% CI)]
Clinical Remission [Clinical remission was defined as Mayo stool frequency subscore of 0 or 1, Mayo rectal bleeding subscore of 0, and Mayo endoscopy subscore of 0 or 1 (modified so that 1 does not include friability).] | 22 | 7% | 62 | 19% | 12% (7%, 18%) [p < 0.001]
Bio-naïve [An additional 7 subjects on placebo and 9 subjects on ustekinumab (6 mg/kg) had been exposed to, but had not failed, biologics.] | 14/151 | 9% | 36/147 | 24%
Prior biologic failure | 7/161 | 4% | 24/166 | 14%
Endoscopic Improvement [Endoscopic improvement was defined as Mayo endoscopy subscore of 0 or 1 (modified so that 1 does not include friability).] | 40 | 13% | 80 | 25% | 12% (6%, 19%)
Bio-naïve | 28/151 | 19% | 43/147 | 29%
Prior biologic failure | 11/161 | 7% | 34/166 | 20%
Clinical Response [Clinical response was defined as a decrease from baseline in the modified Mayo score by ≥30% and ≥2 points, with either a decrease from baseline in the rectal bleeding subscore ≥1 or a rectal bleeding subscore of 0 or 1.] | 99 | 31% | 186 | 58% | 27% (18%, 35%)
Bio-naïve | 55/151 | 36% | 94/147 | 64%
Prior biologic failure | 42/161 | 26% | 86/166 | 52%
Histologic-Endoscopic Mucosal Improvement [Histologic-endoscopic mucosal improvement was defined as combined endoscopic improvement (Mayo endoscopy subscore of 0 or 1) and histologic improvement of the colon tissue (neutrophil infiltration in <5% of crypts, no crypt destruction, and no erosions, ulcerations, or granulation tissue).] | 26 | 8% | 54 | 17% | 9% (3%, 14%)
Bio-naïve | 19/151 | 13% | 30/147 | 20%
Prior biologic failure | 6/161 | 4% | 21/166 | 13%

The relationship of histologic-endoscopic mucosal improvement, as defined in UC-1, at Week 8 to disease progression and long-term outcomes was not evaluated during UC-1.

Rectal Bleeding and Stool Frequency Subscores

Decreases in rectal bleeding and stool frequency subscores were observed as early as Week 2 in ustekinumab-treated subjects.

Trial UC-2

The maintenance trial (UC-2) evaluated 523 subjects who achieved clinical response 8 weeks following the intravenous administration of either induction dose of ustekinumab in UC-1. These subjects were randomized to receive a subcutaneous maintenance regimen of either 90 mg ustekinumab every 8 weeks, or every 12 weeks (a lower dose than recommended), or placebo for 44 weeks.

The primary endpoint was the proportion of subjects in clinical remission at Week 44. The secondary endpoints included the proportion of subjects maintaining clinical response at Week 44, the proportion of subjects with endoscopic improvement at Week 44, the proportion of subjects with corticosteroid-free clinical remission at Week 44, and the proportion of subjects maintaining clinical remission at Week 44 among subjects who achieved clinical remission 8 weeks after induction.

Results of the primary and secondary endpoints at Week 44 in subjects treated with ustekinumab at the recommended dosage (90 mg every 8 weeks) compared to the placebo are shown in Table 16.

Table 16: Efficacy Endpoints of Maintenance at Week 44 in UC-2 (52 Weeks from Initiation of the Induction Dose)
 | Placebo [The placebo group consisted of subjects who were in response to ustekinumab and were randomized to receive placebo at the start of maintenance therapy.] N = 175 [Clinical response was defined as a decrease from baseline in the modified Mayo score by ≥30% and ≥2 points, with either a decrease from baseline in the rectal bleeding subscore ≥1 or a rectal bleeding subscore of 0 or 1.] |  | 90 mg ustekinumab every 8 weeks N = 176 |  | Treatment difference and 95% CI
Endpoint | N | % | N | % | Treatment difference and 95% CI
Clinical Remission [Clinical remission was defined as Mayo stool frequency subscore of 0 or 1, Mayo rectal bleeding subscore of 0, and Mayo endoscopy subscore of 0 or 1 (modified so that 1 does not include friability).] | 46 | 26% | 79 | 45% | 19% (9%, 28%) [p =<0.001]
Bio-naïve [An additional 3 subjects on placebo and 6 subjects on ustekinumab had been exposed to, but had not failed, biologics.] | 30/84 | 36% | 39/79 | 49%
Prior biologic failure | 16/88 | 18% | 37/91 | 41%
Maintenance of Clinical Response at Week 44 | 84 | 48% | 130 | 74% | 26% (16%, 36%)
Bio-naïve | 49/84 | 58% | 62/79 | 78%
Prior biologic failure | 35/88 | 40% | 64/91 | 70%
Endoscopic Improvement [Endoscopic improvement was defined as Mayo endoscopy subscore of 0 or 1 (modified so that 1 does not include friability).] | 47 | 27% | 83 | 47% | 20% (11%, 30%)
Bio-naïve | 29/84 | 35% | 42/79 | 53%
Prior biologic failure | 18/88 | 20% | 38/91 | 42%
Corticosteroid-free Clinical Remission [Corticosteroid-free clinical remission was defined as subjects in clinical remission and not receiving corticosteroids at Week 44.] | 45 | 26% | 76 | 43% | 17% (8%, 27%)
Bio-naïve | 30/84 | 36% | 38/79 | 48%
Prior biologic failure | 15/88 | 17% | 35/91 | 38%
Maintenance of Clinical Remission at Week 44 in subjects who achieved clinical remission 8 weeks after induction | 18/50 | 36% | 27/41 | 66% | 31% (12%, 50%) [p=0.004]
Bio-naïve | 12/27 | 44% | 14/20 | 70%
Prior biologic failure | 6/23 | 26% | 12/18 | 67%

Other Endpoints

Week 16 Responders to Ustekinumab Induction

Subjects who were not in clinical response 8 weeks after induction with ustekinumab in UC- 1 were not included in the primary efficacy analyses for trial UC-2; however, these subjects were eligible to receive a 90 mg subcutaneous injection of ustekinumab at Week 8. Of these subjects, 55/101 (54%) achieved clinical response eight weeks later (Week 16) and received ustekinumab 90 mg subcutaneously every 8 weeks during the UC-2 trial. At Week 44, there were 97/157 (62%) subjects who maintained clinical response and there were 51/157 (32%) who achieved clinical remission.

Histologic-Endoscopic Mucosal Improvement at Week 44

The proportion of subjects achieving histologic-endoscopic mucosal improvement during maintenance treatment in UC-2 was 75/172 (44%) among subjects on ustekinumab and 40/172 (23%) in subjects on placebo at Week 44. The relationship of histologic-endoscopic mucosal improvement, as defined in UC-2, at Week 44 to progression of disease or long-term outcomes was not evaluated in UC-2.

Endoscopic Normalization

Normalization of endoscopic appearance of the mucosa was defined as a Mayo endoscopic subscore of 0. At Week 8 in UC-1, endoscopic normalization was achieved in 25/322 (8%) of subjects treated with ustekinumab and 12/319 (4%) of subjects in the placebo group. At Week 44 of UC-2, endoscopic normalization was achieved in 51/176 (29%) of subjects treated with ustekinumab and in 32/175 (18%) of subjects in placebo group.

15 REFERENCES

1 Surveillance, Epidemiology, and End Results (SEER) Program (www.seer.cancer.gov) SEER*Stat Database: Incidence - SEER 6.6.2 Regs Research Data, Nov 2009 Sub (1973–2007) - Linked To County Attributes - Total U.S., 1969– 2007 Counties, National Cancer Institute, DCCPS, Surveillance Research Program, Surveillance Systems Branch, released April 2010, based on the November 2009 submission.

16 HOW SUPPLIED/STORAGE AND HANDLING

USTEKINUMAB-TTWE injection is a clear, colorless to light yellow, sterile and preservative-free solution. It is supplied as individually packaged, single-dose prefilled syringe, or single-dose vial.

For Subcutaneous Use

Prefilled Syringes

- 45 mg/0.5 mL (NDC 82009-160-11)
- 90 mg/mL (NDC 82009-162-11)

Each prefilled syringe is equipped with a 29 gauge fixed ½ inch needle, a needle safety guard, and a needle cover that is not made with natural rubber latex.

Single-dose Vial

- 45 mg/0.5 mL (NDC 82009-161-94)

For Intravenous Infusion

Single-dose Vial

- 130 mg/26 mL (5 mg/mL) (NDC 82009-163-94)

Storage and Stability

Store USTEKINUMAB-TTWE vials, and prefilled syringes refrigerated between 2°C to 8°C (36°F to 46°F). Store USTEKINUMAB-TTWE vials upright. Keep the product in the original carton to protect from light until the time of use. Do not freeze. Do not shake.

If needed, individual prefilled syringes may be stored at room temperature up to 30°C (86°F) for a maximum single period of up to 35 days in the original carton to protect from light. If not used within 35 days of room temperature storage, discard the prefilled syringe. The prefilled syringe may be returned to the refrigerator one time only for a maximum of 60 days. If not used within 60 days, discard the prefilled syringe. Record the date when the prefilled syringe is removed from and returned to the refrigerator on the carton in the space provided.

Do not use USTEKINUMAB-TTWE after the expiration date on the carton or on the prefilled syringe.

17 PATIENT COUNSELING INFORMATION

Advise the patient and/or caregiver to read the FDA-approved patient labeling (Medication Guide and Instructions for Use).

Infections

Inform patients that USTEKINUMAB-TTWE may lower the ability of their immune system to fight infections and to contact their healthcare provider immediately if they develop any signs or symptoms of infection [see Warnings and Precautions (5.1)].

Malignancies

Inform patients of the risk of developing malignancies while receiving USTEKINUMAB-TTWE [see Warnings and Precautions (5.4)].

Serious Hypersensitivity and Reactions

- Inform patients that serious hypersensitivity reactions have been reported with intravenous and subcutaneous administration of ustekinumab products. Instruct patients to discontinue USTEKINUMAB-TTWE and seek immediate medical attention if they experience any signs or symptoms of hypersensitivity reactions [see Warnings and Precautions (5.5)].

Posterior Reversible Encephalopathy Syndrome (PRES)

Inform patients to immediately contact their healthcare provider if they experience signs and symptoms of PRES (which may include headache, seizures, confusion, or visual disturbances) [see Warnings and Precautions (5.6)].

Immunizations

Inform patients that USTEKINUMAB-TTWE can interfere with the usual response to immunizations and that they should avoid live vaccines [see Warnings and Precautions (5.7)].

Administration

Instruct patients to follow sharps disposal recommendations, as described in the Instructions for Use.

Manufactured by:
Samsung Bioepis Co., Ltd.,
76, Songdogyoyuk-ro, Yeonsu-gu, Incheon, 21987, Republic of Korea
U.S. License No. 2046

Manufactured for:
Quallent Pharmaceuticals Health LLC,
Grand Cayman, Cayman Islands

MEDICATION GUIDE
USTEKINUMAB-TTWE (us-te-KIN-ne-mab ttwe)
injection, for subcutaneous or intravenous use

What is the most important information I should know about USTEKINUMAB-TTWE?
USTEKINUMAB-TTWE is a medicine that affects your immune system. USTEKINUMAB-TTWE can increase your risk of having serious side effects, including:

- Serious infections: USTEKINUMAB-TTWE may lower the ability of your immune system to fight infections and may increase your risk of infections. Some people have serious infections during treatment with ustekinumab products, including tuberculosis (TB), and infections caused by bacteria, fungi, or viruses. Some people have to be hospitalized for treatment of their infection.
  - Your healthcare provider should check you for TB before starting USTEKINUMAB-TTWE.
  - If your healthcare provider feels that you are at risk for TB, you may be treated with medicine for TB before you begin treatment with USTEKINUMAB-TTWE and during treatment with USTEKINUMAB-TTWE.
  - Your healthcare provider should watch you closely for signs and symptoms of TB while you are being treated with USTEKINUMAB-TTWE.
    You should not start USTEKINUMAB-TTWE if you have any kind of infection unless your healthcare provider says it is okay.
    Before starting USTEKINUMAB-TTWE, tell your healthcare provider if you:
  - think you have an infection or have symptoms of an infection such as:

- fever, sweat, or chills
- muscle aches
- cough
- shortness of breath
- blood in phlegm

- weight loss
- warm, red, or painful skin or sores on your body
- diarrhea or stomach pain
- burning when you urinate or urinate more often than normal
- feel very tired

- are being treated for an infection or have any open cuts.
- get a lot of infections or have infections that keep coming back.
- have TB or have been in close contact with someone with TB.

After starting USTEKINUMAB-TTWE, call your healthcare provider right away if you have any symptoms of an infection (see above). These may be signs of infections such as chest infections, or skin infections or shingles that could have serious complications. USTEKINUMAB-TTWE can make you more likely to get infections or make an infection that you have worse.

- People who have a genetic problem where the body does not make any of the proteins interleukin 12 (IL-12) and interleukin 23 (IL-23) are at a higher risk for certain serious infections. These infections can spread throughout the body and cause death. People who take USTEKINUMAB-TTWE may also be more likely to get these infections.
- Cancers. USTEKINUMAB-TTWE may decrease the activity of your immune system and increase your risk for certain types of cancers. Tell your healthcare provider if you have ever had any type of cancer. Some people who are receiving ustekinumab products and have risk factors for skin cancer have developed certain types of skin cancers. During your treatment with USTEKINUMAB-TTWE, tell your healthcare provider if you develop any new skin growths.

What is USTEKINUMAB-TTWE?
USTEKINUMAB-TTWE is a prescription medicine used to treat:

- adults and children 6 years of age and older with moderate to severe plaque psoriasis who may benefit from taking injections or pills (systemic therapy) or phototherapy (treatment using ultraviolet light alone or with pills).
- adults and children 6 years of age and older with active psoriatic arthritis.
- adults with moderately to severely active Crohn's disease.
- adults with moderately to severely active ulcerative colitis.

It is not known if USTEKINUMAB-TTWE is safe and effective in children with Crohn's disease or ulcerative colitis or in children less than 6 years of age with plaque psoriasis or psoriatic arthritis.

Who should not use USTEKINUMAB-TTWE?
Do not use USTEKINUMAB-TTWE if you are allergic to ustekinumab products or any of the ingredients in USTEKINUMAB-TTWE. See the end of this Medication Guide for a complete list of ingredients in USTEKINUMAB-TTWE.

Before you use or receive USTEKINUMAB-TTWE, tell your healthcare provider about all of your medical conditions, including if you:

- have any of the conditions or symptoms listed in the section "What is the most important information I should know about USTEKINUMAB-TTWE?"
- ever had an allergic reaction to ustekinumab products. Ask your healthcare provider if you are not sure.
- have recently received or are scheduled to receive an immunization (vaccine). People who are being treated with USTEKINUMAB-TTWE should avoid receiving live vaccines. Tell your healthcare provider if anyone in your house needs a live vaccine. The viruses used in some types of live vaccines can spread to people with a weakened immune system and can cause serious problems. You should avoid receiving the BCG vaccine during the one year before receiving USTEKINUMAB-TTWE or one year after you stop receiving USTEKINUMAB-TTWE.
- have any new or changing lesions within psoriasis areas or on normal skin.
- are receiving or have received allergy shots, especially for serious allergic reactions. Allergy shots may not work as well for you during treatment with USTEKINUMAB-TTWE. USTEKINUMAB-TTWE may also increase your risk of having an allergic reaction to an allergy shot.
- receive or have received phototherapy for your psoriasis.
- are pregnant or plan to become pregnant. It is not known if USTEKINUMAB-TTWE can harm your unborn baby.
  You and your healthcare provider should decide if you will receive USTEKINUMAB-TTWE.
- are breastfeeding or plan to breastfeed. USTEKINUMAB-TTWE can pass into your breast milk.
- Talk to your healthcare provider about the best way to feed your baby if you receive USTEKINUMAB-TTWE.

Tell your healthcare provider about all the medicines you take, including prescription and over-the-counter medicines, vitamins, and herbal supplements.
Know the medicines you take. Keep a list of them to show your healthcare provider and pharmacist when you get a new medicine.

How should I use USTEKINUMAB-TTWE?

- Use USTEKINUMAB-TTWE exactly as your healthcare provider tells you to. The healthcare provider will determine the right dose of USTEKINUMAB-TTWE, the amount for each injection, and how often it should be given. Be sure to keep all scheduled follow-up appointments.
- Adults with Crohn's disease and ulcerative colitis will receive the first dose of USTEKINUMAB-TTWE through a vein in the arm (intravenous infusion) in a healthcare facility by a healthcare provider. It takes at least 1 hour to receive the full dose of medicine. USTEKINUMAB-TTWE will then be received as an injection under the skin (subcutaneous injection) 8 weeks after the first dose of USTEKINUMAB-TTWE, as described below.
- Adults and children 6 years of age and older with plaque psoriasis or psoriatic arthritis will receive USTEKINUMAB-TTWE as an injection under the skin as described below.
- Injecting USTEKINUMAB-TTWE under the skin
  - USTEKINUMAB-TTWE is intended for use under the guidance and supervision of a healthcare provider.
  - In children, it is recommended that USTEKINUMAB-TTWE be administered by a healthcare provider. If a healthcare provider decides that you or a caregiver may give the injections of USTEKINUMAB-TTWE at home, you or a caregiver should receive training on the right way to prepare and give the injections.
  - Do not try to inject USTEKINUMAB-TTWE until you have been shown how to give the injections by a healthcare provider.
  - USTEKINUMAB-TTWE can be injected under the skin in the upper arms, buttocks, upper legs (thighs) or stomach area (abdomen).
  - Do not give an injection in an area of the skin that is tender, bruised, red or hard.
  - Use a different injection site each time you use USTEKINUMAB-TTWE.
- If you inject too much USTEKINUMAB-TTWE, call the healthcare provider or Poison Help line at 1-800-222-1222, or go to the nearest emergency room right away.

Read the detailed Instructions for Use at the end of this Medication Guide for instructions about how to prepare and inject a dose of USTEKINUMAB-TTWE, and how to properly throw away (dispose of) used needles, syringes, and vials. The syringe, needle, and vial must never be re-used. After the rubber stopper is punctured, USTEKINUMAB-TTWE can become contaminated by harmful bacteria which could cause an infection if re-used. Therefore, throw away any unused portion of USTEKINUMAB-TTWE.

What should I avoid while using USTEKINUMAB-TTWE?
You should avoid receiving a live vaccine during treatment with USTEKINUMAB-TTWE. See "Before you use or receive USTEKINUMAB-TTWE, tell your healthcare provider about all of your medical conditions, including if you:"

What are the possible side effects of USTEKINUMAB-TTWE?
USTEKINUMAB-TTWE may cause serious side effects, including:

- See "What is the most important information I should know about USTEKINUMAB-TTWE?"
- Serious allergic reactions. Serious allergic reactions including death can occur with USTEKINUMAB-TTWE. Stop using USTEKINUMAB-TTWE and get medical help right away if you get any of the following symptoms of a serious allergic reaction:

- feeling faint
- swelling of your face, eyelids, tongue, or throat
- chest discomfort

- trouble breathing
- skin rash

- Posterior Reversible Encephalopathy Syndrome (PRES). PRES is a rare condition that affects the brain and can cause death. Tell your healthcare provider right away if you get any symptoms of PRES during treatment with USTEKINUMAB-TTWE, including:

- headache
- seizures

- confusion
- vision problems

- Lung inflammation. Cases of lung inflammation have happened in some people who receive ustekinumab products, and may be serious. These lung problems may need to be treated in a hospital. Tell your healthcare provider right away if you develop shortness of breath or a cough that doesn't go away during treatment with USTEKINUMAB-TTWE.

The most common side effects of USTEKINUMAB-TTWE include:

- nasal congestion, sore throat, and runny nose
- upper respiratory infections
- fever
- headache
- tiredness
- itching
- nausea and vomiting
- influenza

- redness at the injection site
- vaginal yeast infections
- urinary tract infections
- sinus infection
- bronchitis
- diarrhea
- stomach pain
- joint pain

These are not all of the possible side effects of USTEKINUMAB-TTWE. Call your doctor for medical advice about side effects. You may report side effects to FDA at 1-800-FDA-1088.
You may also report side effects to Quallent Pharmaceuticals Health LLC at 1-877-605-7243.

How should I store USTEKINUMAB-TTWE?

- Store USTEKINUMAB-TTWE vials, and prefilled syringes in a refrigerator between 36°F to 46°F (2°C to 8°C).
- Store USTEKINUMAB-TTWE vials standing up straight (upright).
- Store USTEKINUMAB-TTWE in the original carton to protect it from light until time to use it.
- Do not freeze USTEKINUMAB-TTWE.
- Do not shake USTEKINUMAB-TTWE.
- If needed, individual USTEKINUMAB-TTWE prefilled syringes may be stored at room temperature up to 86°F (30°C) for a maximum single period of up to 35 days in the original carton to protect from light.
- Record the date when the prefilled syringe is first removed from the refrigerator on the carton in the space provided.
- You may return the prefilled syringe to the refrigerator 1 time only for a maximum of 60 days, either during the 35-day period or at the end of the 35-day period.
- Record the date when the prefilled syringe is returned to the refrigerator on the carton.
- Throw away (discard) the prefilled syringe if not used within 35 days of room temperature storage and you did not return it to the refrigerator, or if it has been returned to the refrigerator and is not used within 60 days.
- Do not use USTEKINUMAB-TTWE after the expiration date on the carton or on the prefilled syringe.

Keep USTEKINUMAB-TTWE and all medicines out of the reach of children.

General information about the safe and effective use of USTEKINUMAB-TTWE.
Medicines are sometimes prescribed for purposes other than those listed in a Medication Guide. Do not use USTEKINUMAB-TTWE for a condition for which it was not prescribed. Do not give USTEKINUMAB-TTWE to other people, even if they have the same symptoms that you have. It may harm them. You can ask your pharmacist or healthcare provider for information about USTEKINUMAB-TTWE that was written for health professionals.

What are the ingredients in USTEKINUMAB-TTWE?
Active ingredient: ustekinumab-ttwe

Inactive ingredients: Single-dose prefilled syringe, and single-dose vial for subcutaneous use contain histidine, histidine hydrochloride monohydrate, polysorbate 80, and sucrose. Single-dose vial for intravenous infusion contains edetate disodium, histidine, histidine hydrochloride monohydrate, methionine, polysorbate 80, and sucrose.

Manufactured by: Samsung Bioepis Co., Ltd.,
76, Songdogyoyuk-ro, Yeonsu-gu, Incheon, 21987, Republic of Korea
U.S. License No. 2046
Manufactured for: Quallent Pharmaceuticals Health LLC,
Grand Cayman, Cayman Islands

For more information, call 1-877-605-7243.

This Medication Guide has been approved by the U.S. Food and Drug Administration.

Revised: 01/2026

INSTRUCTIONS FOR USE
USTEKINUMAB-TTWE (us-te-KIN-ne-mab ttwe)
injection, for subcutaneous use

This Instructions for Use contains information on how to inject USTEKINUMAB-TTWE using a prefilled syringe.

Read this Instructions for Use before you start using USTEKINUMAB-TTWE. A healthcare provider should show you how to prepare and give an injection of USTEKINUMAB-TTWE the right way.

If you cannot give the injection:

- ask a healthcare provider to help you, or
- ask someone who has been trained by a healthcare provider to give the injections.

Do not try to inject USTEKINUMAB-TTWE until you have been shown how to inject USTEKINUMAB-TTWE by a healthcare provider.

Important information You Need to Know Before Injecting USTEKINUMAB-TTWE:

- For subcutaneous use only (inject directly under the skin)
- Before you start, check the carton to make sure that it is the right dose. You will have either 45 mg or 90 mg as prescribed by the healthcare provider.
  - If the dose is 45 mg, you will receive one 45 mg prefilled syringe.
  - If the dose is 90 mg, you will receive either one 90 mg prefilled syringe or two 45 mg prefilled syringes. If you receive two 45 mg prefilled syringes for a 90 mg dose, you will need to give two injections, one right after the other.
- Check the expiration date on the prefilled syringe and carton. Do not use USTEKINUMAB-TTWE after the expiration date has passed, or if the prefilled syringe has been stored above 86°F (30°C), stored at room temperature up to 86°F (30°C) for longer than 35 days, or returned to the refrigerator and stored for longer than 60 days. Call the healthcare provider or pharmacist, or call Quallent Pharmaceuticals Health LLC at 1-877-605-7243 for help.
- Make sure the syringe is not damaged. Do not use the prefilled syringe if it is damaged.
- Check the prefilled syringe for any particles or discoloration. The liquid in the prefilled syringe should look clear and colorless to light yellow.
- Do not use if it is frozen, discolored, cloudy or has particles. Get a new prefilled syringe.
- Do not shake the prefilled syringe at any time. Shaking the prefilled syringe may damage the USTEKINUMAB-TTWE medicine. If the prefilled syringe has been shaken, do not use it. Get a new prefilled syringe.
- To reduce the risk of accidental needle sticks, each prefilled syringe has a needle guard that is automatically activated to cover the needle after you have given the injection. Do not pull back on the plunger at any time.

Storing USTEKINUMAB-TTWE prefilled syringes

- Store USTEKINUMAB-TTWE prefilled syringes in the refrigerator between 36°F to 46°F (2°C to 8°C).
- Store USTEKINUMAB-TTWE prefilled syringes in the original carton to protect from light until the time of use.
- Do not freeze USTEKINUMAB-TTWE prefilled syringes.
- If needed, individual prefilled syringes may be stored at room temperature up to 86°F (30°C) for a maximum single period of up to 35 days in the original carton to protect from light.
- Record the date when the prefilled syringe is removed from the refrigerator on the carton in the space provided.
- You may return the prefilled syringe to the refrigerator 1 time only for a maximum of 60 days, either during the 35-day period or at the end of the 35-day period.
- Record the date when the prefilled syringe is returned to the refrigerator on the carton.
- Throw away (discard) the prefilled syringe if not used within 35 days of room temperature storage and you did not return it to the refrigerator, or if it has been returned to the refrigerator and is not used within 60 days.

Keep USTEKINUMAB-TTWE and all medicines out of the reach of children.

Gather the supplies you will need to prepare and to give the injection. (See Figure A)

You will need:

- antiseptic wipes
- cotton balls or gauze pads
- adhesive bandage
- your prescribed dose of USTEKINUMAB-TTWE (See Figure B)
- FDA-cleared sharps disposal container. See "Step 4: Disposing of the syringes."

Figure A

Figure B

Step 1: Preparing the injection

- Choose a well-lit, clean, flat work surface.
- Leave USTEKINUMAB-TTWE prefilled syringe at room temperature for about 30 minutes before injecting. Do not warm the prefilled syringe in any other way (for example, do not warm it in a microwave or in hot water).
- Wash your hands well with soap and warm water.
- Hold the prefilled syringe with the covered needle pointing upward.

Step 2: Prepare the injection site

- Choose an injection site around the stomach area (abdomen), buttocks, upper legs (thighs). If a caregiver is giving the injection, the outer area of the upper arms may also be used. (See Figure C)
- Use a different injection site for each injection. Do not give an injection in an area of the skin that is tender, bruised, red or hard.
- Clean the skin with an antiseptic wipe where you plan to give the injection.
- Do not touch this area again before giving the injection. Let the skin dry before injecting.
- Do not fan or blow on the clean area.

Figure C

*Areas in gray are recommended injection sites.

Step 3: Injecting USTEKINUMAB-TTWE

- Remove the needle cover when you are ready to inject USTEKINUMAB-TTWE.
- Do not touch the plunger or plunger head while removing the needle cover.
- Hold the body of the prefilled syringe with one hand, and pull the needle cover straight off. (See Figure D)
- Put the needle cover in the trash.
- You may also see a drop of liquid at the end of the needle. This is normal.
- Do not touch the needle or let it touch anything.
- Do not use the prefilled syringe if it is dropped without the needle cover in place.

Figure D

- Hold the body of the prefilled syringe in one hand between the thumb and index fingers. (See Figure E)

Figure E

- Do not pull back on the plunger at any time.
- Use the other hand to gently pinch the cleaned area of skin. Hold firmly.
- Use a quick, dart-like motion to insert the needle into the pinched skin at about a 45-degree angle. (See Figure F)

Figure F

- Inject all of the liquid by using your thumb to push in the plunger until the plunger head is completely between the needle guard wings. (See Figure G)

Figure G

- When the plunger is pushed as far as it will go, keep pressure on the plunger head. Take the needle out of the skin and then let go of the skin.
- Slowly take your thumb off the plunger head. This will let the empty syringe move up until the entire needle is covered by the needle guard. (See Figure H)

Figure H

- When the needle is pulled out of the skin, there may be a little bleeding at the injection site. This is normal. You can press a cotton ball or gauze pad to the injection site if needed. Do not rub the injection site. You may cover the injection site with a small adhesive bandage, if necessary.

If the dose is 90 mg, you will receive either one 90 mg prefilled syringe or two 45 mg prefilled syringes. If you receive two 45 mg prefilled syringes for a 90 mg dose, you will need to give a second injection right after the first. Repeat Steps 1 to 3 for the second injection using a new syringe. Choose a different site for the second injection.

Step 4: Disposing of the syringes.

- Put the syringe in an FDA-cleared sharps disposal container right away after use. Do not throw away (dispose of) syringes in your household trash.
- If you do not have an FDA-cleared sharps disposal container, you may use a household container that is:
  - made of heavy-duty plastic,
  - can be closed with a tight-fitting, puncture-resistant lid, without sharps being able to come out,
  - upright and stable during use,
  - leak-resistant,
  - and properly labeled to warn of hazardous waste inside the container.
- When your sharps disposal container is almost full, you will need to follow your community guidelines for the right way to dispose of your sharps disposal container. There may be local or state laws about how to throw away syringes and needles. For more information about safe sharps disposal, and for specific information about sharps disposal in the state that you live in, go to the FDA's website at: http://www.fda.gov/safesharpsdisposal.
- Do not dispose of your sharps disposal container in your household trash unless your community guidelines permit this. Do not recycle your sharps disposal container.
- If you have any questions, talk to your healthcare provider or pharmacist.

Manufactured by:
Samsung Bioepis Co., Ltd.,
76, Songdogyoyuk-ro, Yeonsu-gu, Incheon, 21987, Republic of Korea
U.S. License No. 2046

Manufactured for:
Quallent Pharmaceuticals Health LLC,
Grand Cayman, Cayman Islands

This Instructions for Use has been approved by the U.S. Food and Drug Administration.
Revised: 01/2026

INSTRUCTIONS FOR USE
USTEKINUMAB-TTWE (us-te-KIN-ne-mab ttwe)
injection, for subcutaneous use

This Instructions for Use contains information on how to inject USTEKINUMAB-TTWE using a vial.

Read this Instructions for Use before you start using USTEKINUMAB-TTWE. A healthcare provider should show you how to prepare, measure the dose, and give an injection of USTEKINUMAB-TTWE the right way.

If you cannot give the injection:

- ask a healthcare provider to help you, or
- ask someone who has been trained by a healthcare provider to give the injections.

Do not try to inject USTEKINUMAB-TTWE until you have been shown how to inject USTEKINUMAB-TTWE by a healthcare provider.

Important information You Need to Know Before Injecting USTEKINUMAB-TTWE:

- For subcutaneous use only (inject directly under the skin)
- Before you start, check the carton to make sure that it is the right dose. You will have either 45 mg or 90 mg as prescribed by the healthcare provider.
  - If the dose is 45 mg or less you will receive one 45 mg vial.
  - If the dose is 90 mg, you will receive two 45 mg vials and you will need to give two injections, one right after the other.
- Check the expiration date on the vial and carton. If the expiration date has passed, do not use it. If the expiration date has passed, call the healthcare provider or pharmacist, or call Quallent Pharmaceuticals Health LLC at 1-877-605-7243 for help.
- Check the vial for any particles or discoloration. The liquid in the vial should look clear and colorless to light yellow.
- Do not use if it is frozen, discolored, cloudy or has particles. Get a new vial.
- Do not shake the vial at any time. Shaking the vial may damage the USTEKINUMAB-TTWE medicine. If the vial has been shaken, do not use it. Get a new vial.
- Do not use a USTEKINUMAB-TTWE vial more than one time, even if there is medicine left in the vial. After the rubber stopper is punctured, USTEKINUMAB-TTWE can become contaminated by harmful bacteria which could cause an infection if re-used. Therefore, throw away any unused USTEKINUMAB-TTWE after you give the injection.
- Safely throw away (dispose of) USTEKINUMAB-TTWE vials, needles, and syringes after use. See "Step 6: Disposing of needles, syringes, and vials."
- Do not re-use syringes or needles.
- To avoid needle-stick injuries, do not recap needles.

Storing USTEKINUMAB-TTWE vials

- Store USTEKINUMAB-TTWE vials in a refrigerator between 36°F to 46°F (2°C to 8°C).
- Store USTEKINUMAB-TTWE vials standing up straight (upright).
- Store USTEKINUMAB-TTWE vials in the original carton to protect from light until the time of use.
- Do not freeze USTEKINUMAB-TTWE vials.

Keep USTEKINUMAB-TTWE and all medicines out of the reach of children.

Gather the supplies you will need to prepare USTEKINUMAB-TTWE and to give the injection. (See Figure A)

You will need:

- a syringe with the needle attached, you will need a prescription from a healthcare provider to get syringes with the needles attached from a pharmacy.
- antiseptic wipes
- cotton balls or gauze pads
- adhesive bandage
- your prescribed dose of USTEKINUMAB-TTWE
- FDA-cleared sharps disposal container. See "Step 6: Disposing of needles, syringes, and vials."

Figure A

Step 1: Preparing the injection.

- Choose a well-lit, clean, flat work surface.
- Wash your hands well with soap and warm water.

Step 2: Preparing your injection site

- Choose an injection site around the stomach area (abdomen), buttocks, and upper legs (thighs).
- If a caregiver is giving the injection, the outer area of the upper arms may also be used. (See Figure B)
- Use a different injection site for each injection. Do not give an injection in an area of the skin that is tender, bruised, red or hard.
- Clean the skin with an antiseptic wipe where you plan to give the injection.
- Do not touch this area again before giving the injection. Let the skin dry before injecting.
- Do not fan or blow on the clean area.

Figure B

*Areas in gray are recommended injection sites.

Step 3: Preparing the vial.

- Remove the cap from the top of the vial. Throw away the cap but do not remove the rubber stopper. (See Figure C)

Figure C

- Clean the rubber stopper with an antiseptic wipe. (See Figure D)

Figure D

- Do not touch the rubber stopper after you clean it.
- Put the vial on a flat surface.

Step 4: Preparing the syringe

- Pick up the syringe with the needle attached.
- Remove the cap that covers the needle. (See Figure E)
- Throw the needle cap away. Do not touch the needle or allow the needle to touch anything.

Figure E

- Carefully pull back on the plunger to the line that matches the dose prescribed by the healthcare provider.
- Hold the vial between your thumb and index (pointer) finger.
- Use your other hand to push the syringe needle through the center of the rubber stopper. (See Figure F)

Figure F

- Push down on the plunger until all of the air has gone from the syringe into the vial.
- Turn the vial and the syringe upside down. (See Figure G)
- Hold the USTEKINUMAB-TTWE vial with one hand.
- It is important that the needle is always in the liquid in order to prevent air bubbles forming in the syringe.
- Pull back on the syringe plunger with your other hand.
- Fill the syringe until the black tip of the plunger lines up with the mark that matches the prescribed dose.

Figure G

- Do not remove the needle from the vial. Hold the syringe with the needle pointing up to see if it has any air bubbles inside.
- If there are air bubbles, gently tap the side of the syringe until the air bubbles rise to the top. (See Figure H)
- Slowly press the plunger up until all of the air bubbles are out of the syringe (but none of the liquid is out).
- Remove the syringe from the vial. Do not lay the syringe down or allow the needle to touch anything.

Figure H

Step 5: Injecting USTEKINUMAB-TTWE

- Hold the barrel of the syringe in one hand, between the thumb and index fingers.
- Do not pull back on the plunger at any time.
- Use the other hand to gently pinch the cleaned area of skin. Hold firmly.
- Use a quick, dart-like motion to insert the needle into the pinched skin at about a 45-degree angle. (See Figure I)

Figure I

- Push the plunger with your thumb as far as it will go to inject all of the liquid. Push it slowly and evenly, keeping the skin gently pinched.
- When the syringe is empty, pull the needle out of the skin and then let go of the skin. (See Figure J)

Figure J

- When the needle is pulled out of the skin, there may be a little bleeding at the injection site. This is normal. You can press a cotton ball or gauze pad to the injection site if needed. Do not rub the injection site. You may cover the injection site with a small adhesive bandage, if necessary.

If the dose is 90 mg, you will receive two 45 mg vials and you will need to give a second injection right after the first. Repeat Steps 1 to 5 using a new syringe. Choose a different site for the second injection.

Step 6: Disposing of needles, syringes, and vials.

- Do not re-use a syringe or needle.
- To avoid needle-stick injuries, do not recap a needle.
- Put the needles and syringes in an FDA-cleared sharps disposal container right away after use.
  Do not throw away (dispose of) needles and syringes in your household trash.
- If you do not have an FDA-cleared sharps disposal container, you may use a household container that is:
  - made of heavy-duty plastic
  - can be closed with a tight-fitting, puncture-resistant lid, without sharps being able to come out
  - upright and stable during use
  - leak-resistant,
  - and properly labeled to warn of hazardous waste inside the container.
- When your sharps disposal container is almost full, you will need to follow your community guidelines for the right way to dispose of your sharps disposal container. There may be local or state laws about how to throw away syringes and needles. For more information about safe sharps disposal, and for specific information about sharps disposal in the state that you live in, go to the FDA's website at: http://www.fda.gov/safesharpsdisposal.
- Do not dispose of your sharps disposal container in your household trash unless your community guidelines permit this. Do not recycle your sharps disposal container.
- Throw away the vial into the container where you put the syringes and needles.
- If you have any questions, talk to your healthcare provider or pharmacist.

Manufactured by:
Samsung Bioepis Co., Ltd.,
76, Songdogyoyuk-ro, Yeonsu-gu, Incheon, 21987, Republic of Korea
U.S. License No. 2046

Manufactured for:
Quallent Pharmaceuticals Health LLC,
Grand Cayman, Cayman Islands

This Instructions for Use has been approved by the U.S. Food and Drug Administration.
Revised: 01/2026

45 mg Carton Label

NDC 82009-160-11

Ustekinumab-ttwe

Injection
For subcutaneous use

Contains one 45 mg/0.5 mL syringe
Single-dose prefilled syringe - Discard unused portion
Recommended Dosage: See Prescribing Information
ATTENTION: Dispense the enclosed
Medication Guide to each patient.

Quallent Pharmaceuticals

Rx only

PRINCIPAL DISPLAY PANEL - 45 mg/0.5 mL Vial Label

NDC 82009-161-94

Ustekinumab-ttwe
Injection

45 mg/0.5 mL

For subcutaneous use

Mfd by: Samsung Bioepsis Co., Ltd.

U.S. License No. 2046

PRINCIPAL DISPLAY PANEL - 45 mg/0.5 mL Vial Carton

NDC 82009-161-94

45 mg/
0.5 mL

Ustekinumab-ttwe
Injection

45 mg/0.5 mL

For subcutaneous use

ATTENTION: Dispense the enclosed
Medication Guide to each patient.

One single-dose vial.
Discard unused portion.

Rx only

Quallent
Pharmaceuticals

90 mg Carton Label

NDC 82009-162-11

Ustekinumab-ttwe

Injection
For subcutaneous use

Contains one 90 mg/mL syringe
Single-dose prefilled syringe - Discard unused portion
Recommended Dosage: See Prescribing Information
ATTENTION: Dispense the enclosed
Medication Guide to each patient.

Quallent Pharmaceuticals

Rx only

130 mg Carton Label

NDC 82009-163-94

Ustekinumab-ttwe

Injection

130 mg/26 mL
(5 mg/mL)
For Intravenous
Infusion Only
Must be diluted

ATTENTION: Dispense
the enclosed Medication
Guide to each patient.

One single-dose vial.
Discard unused
portion.

Rx only

Quallent Pharmaceuticals